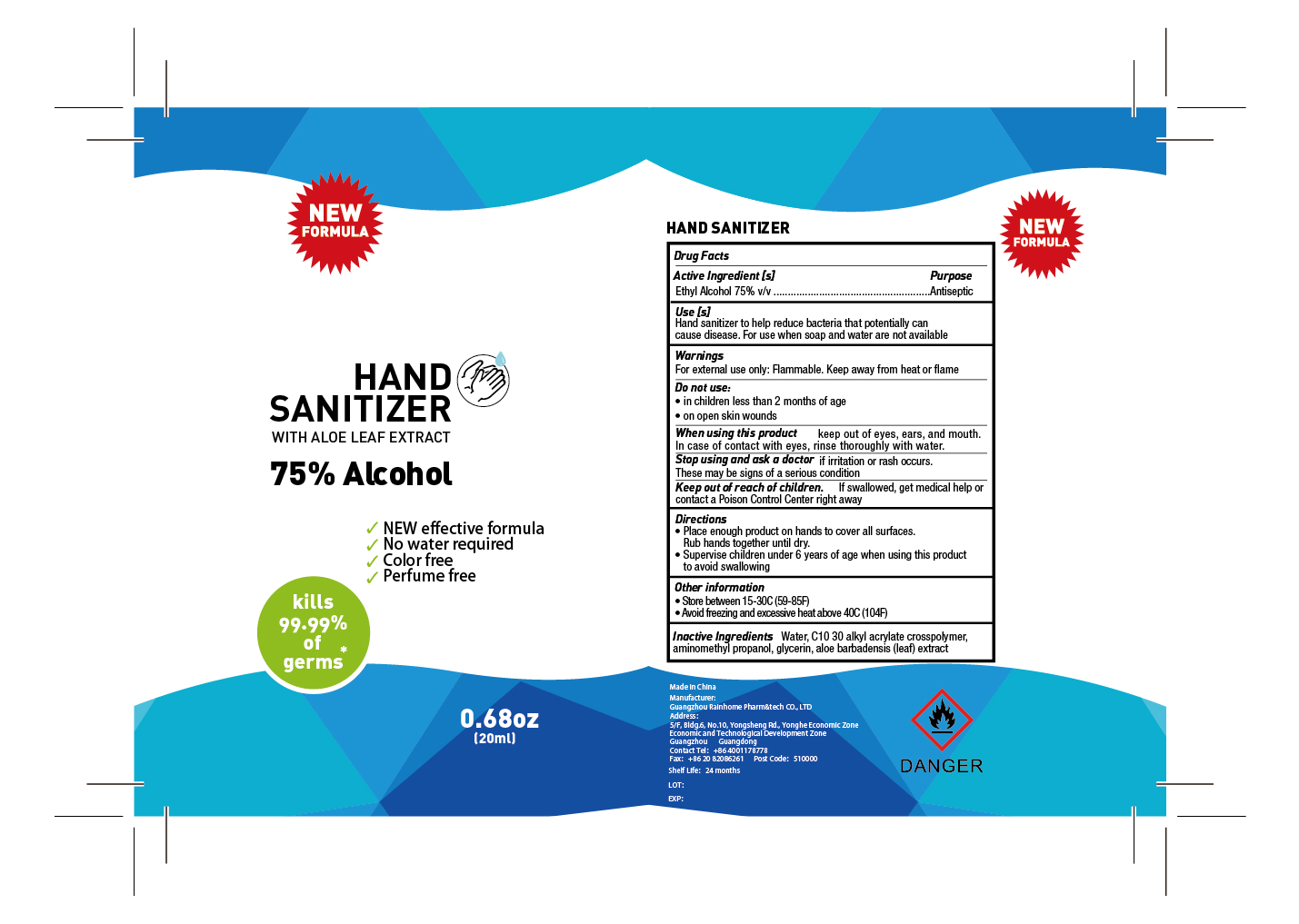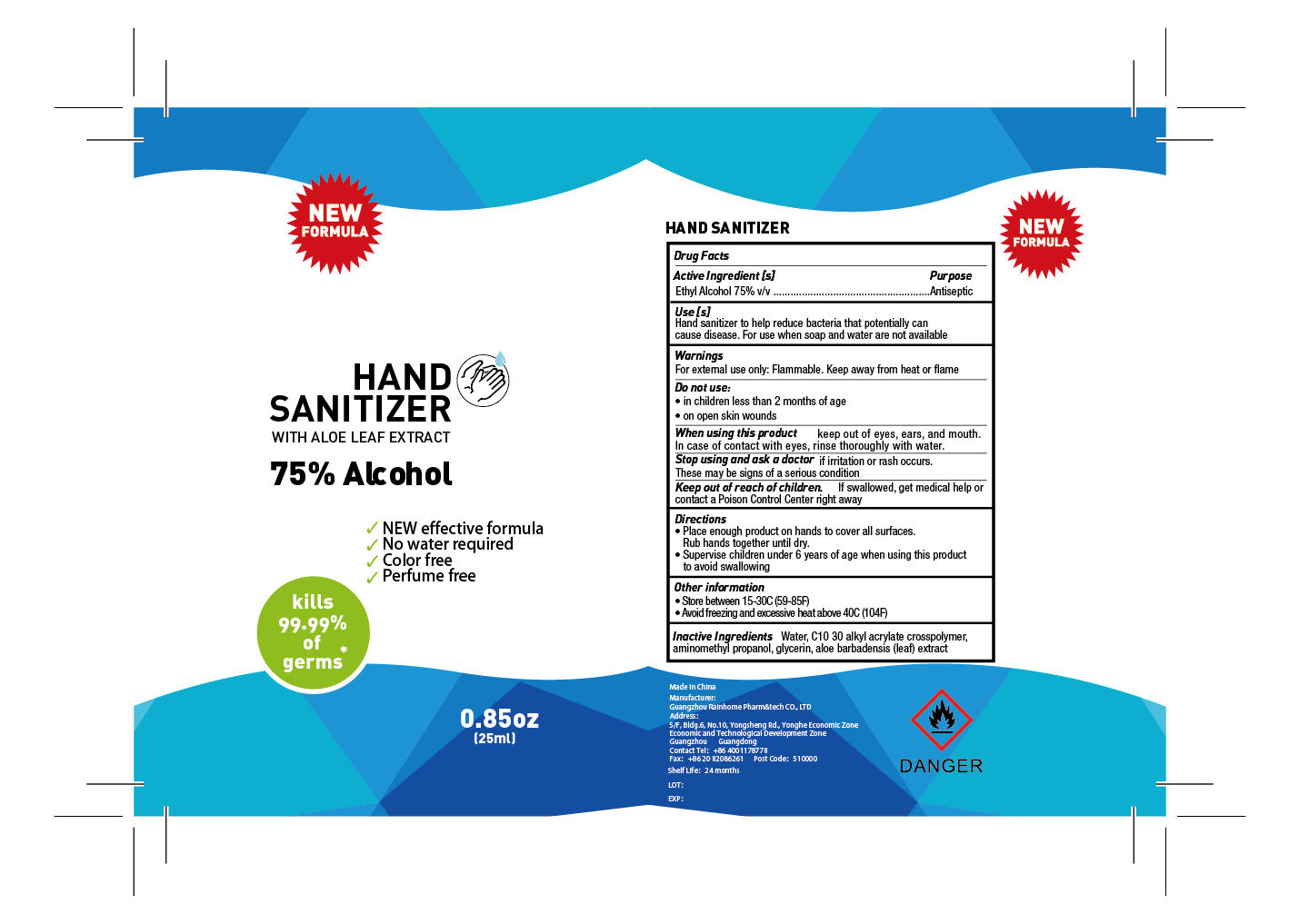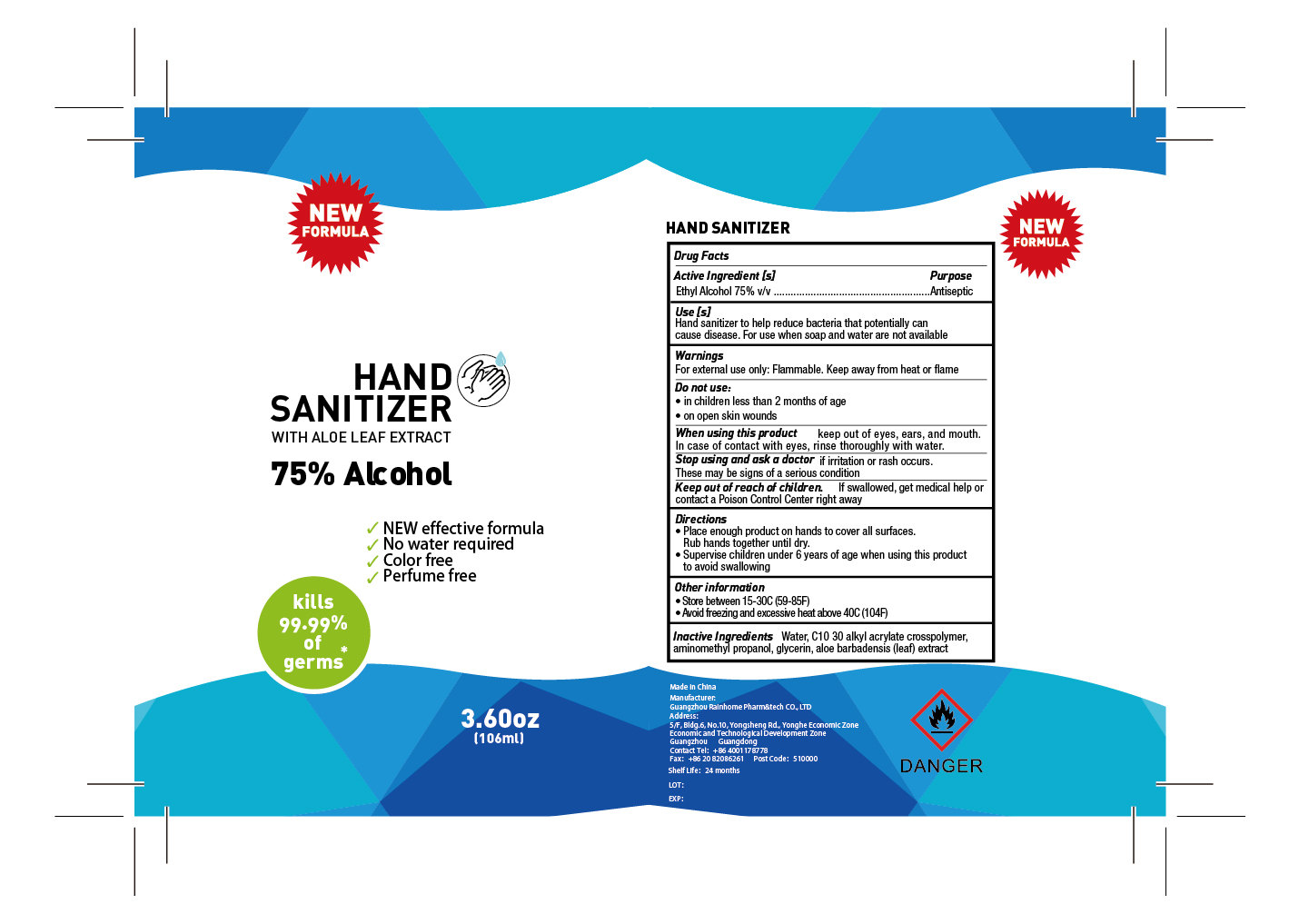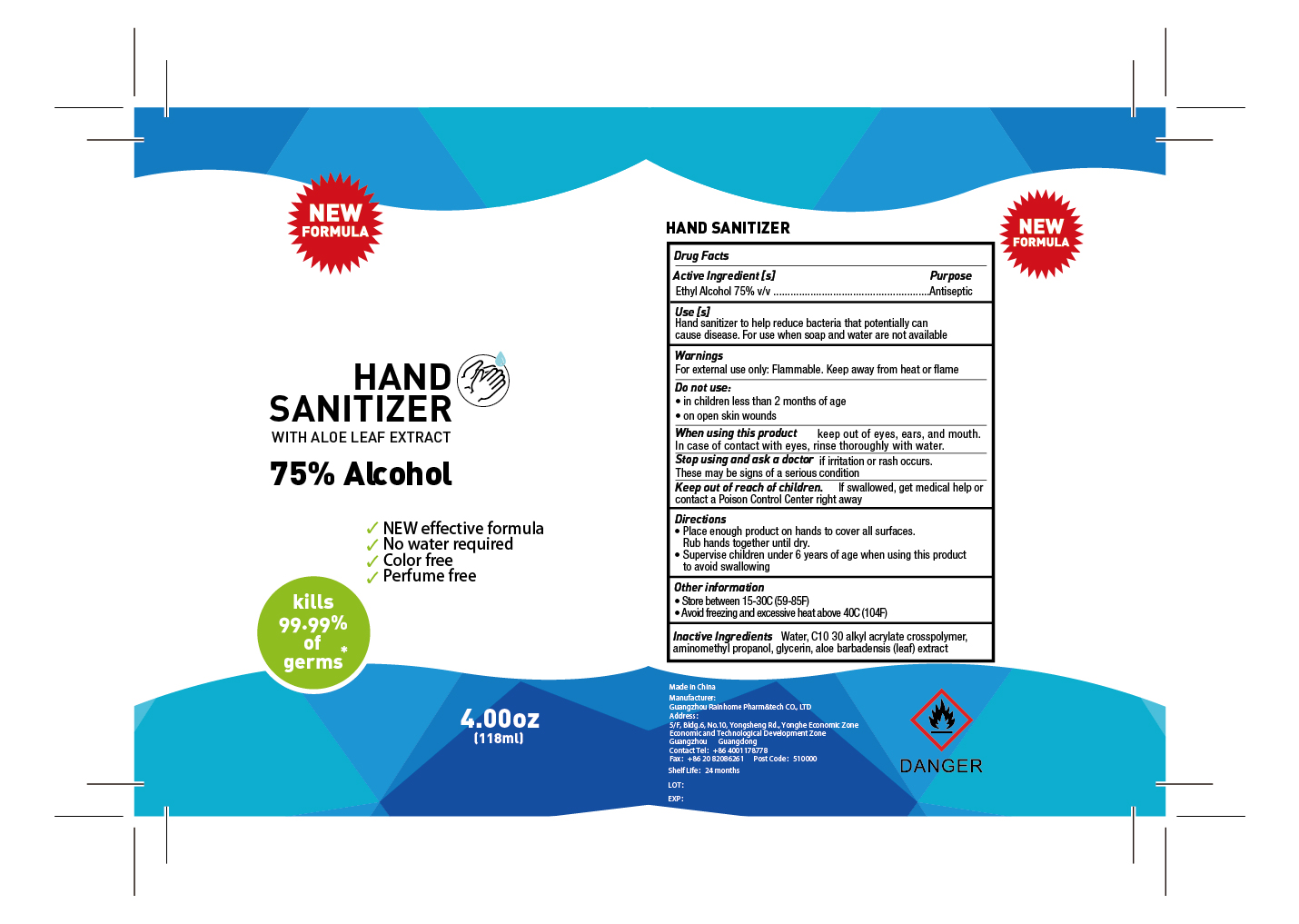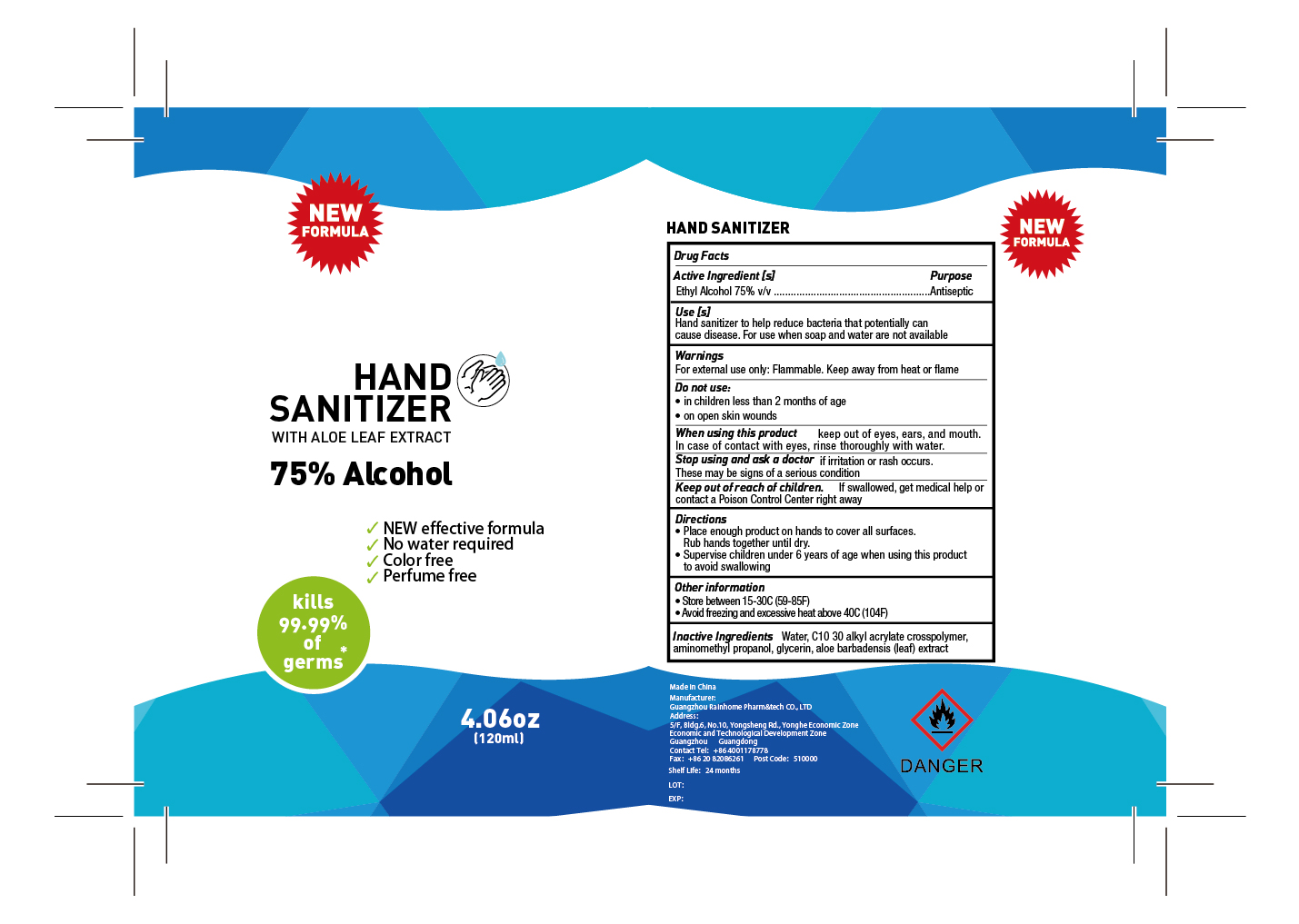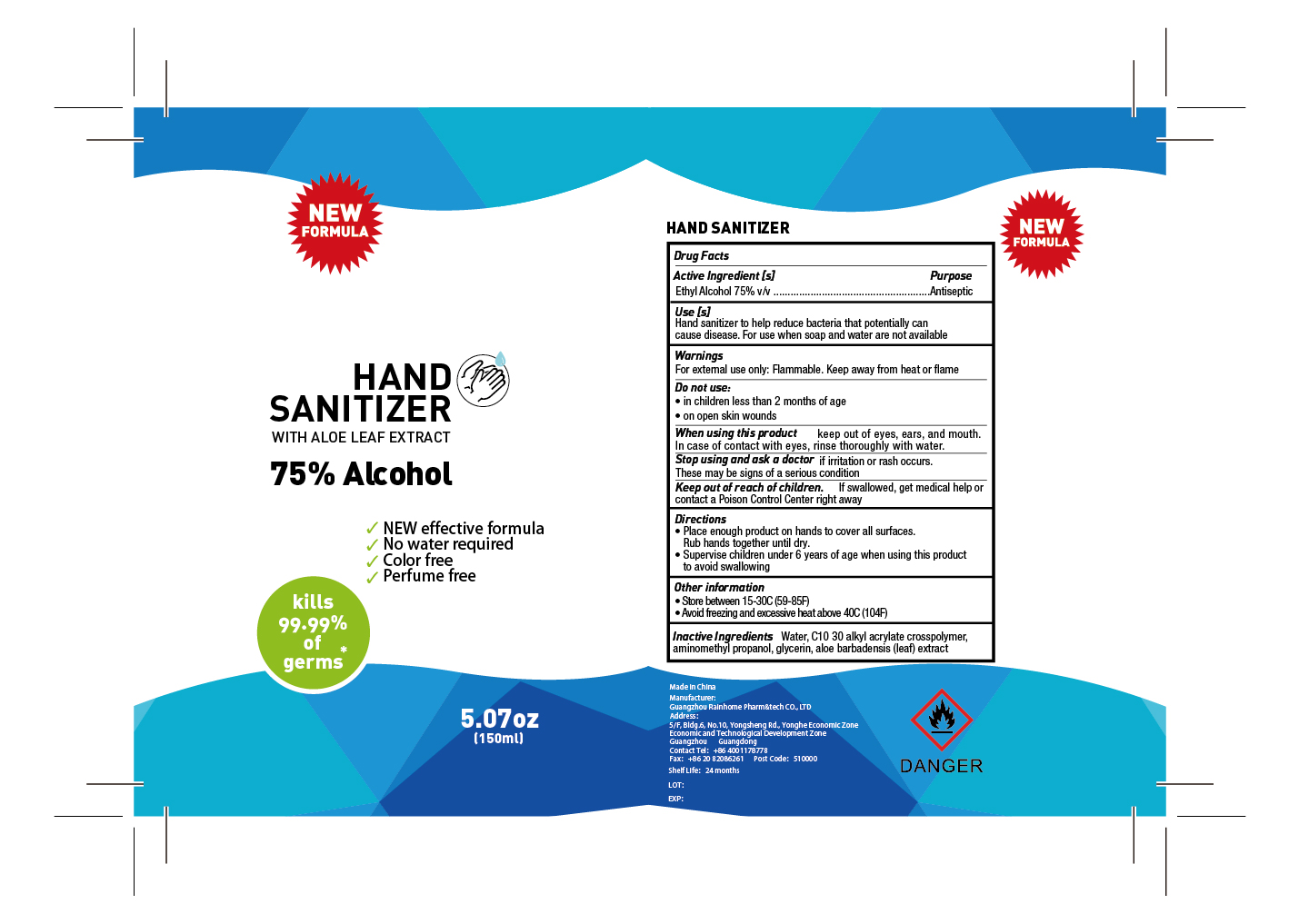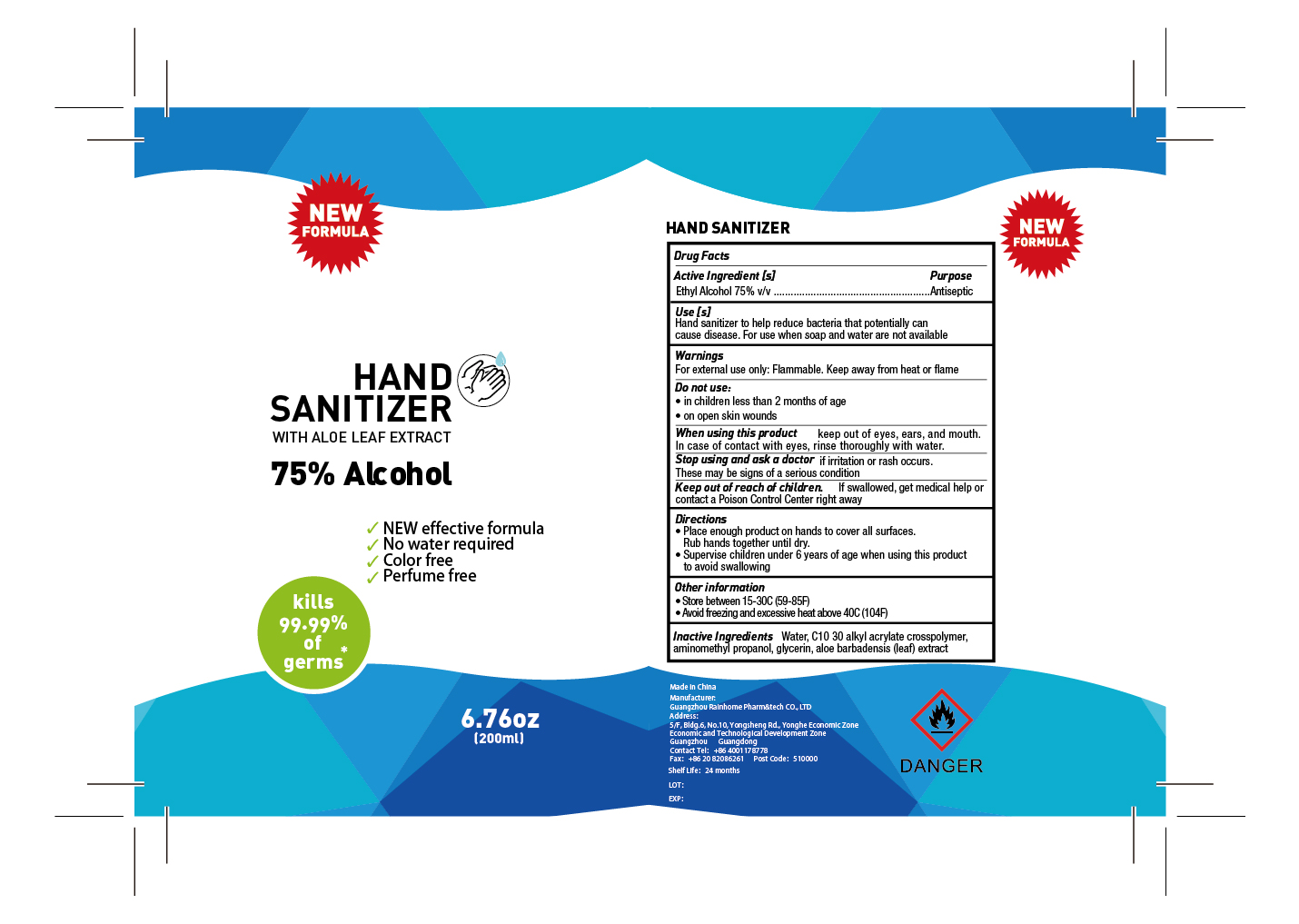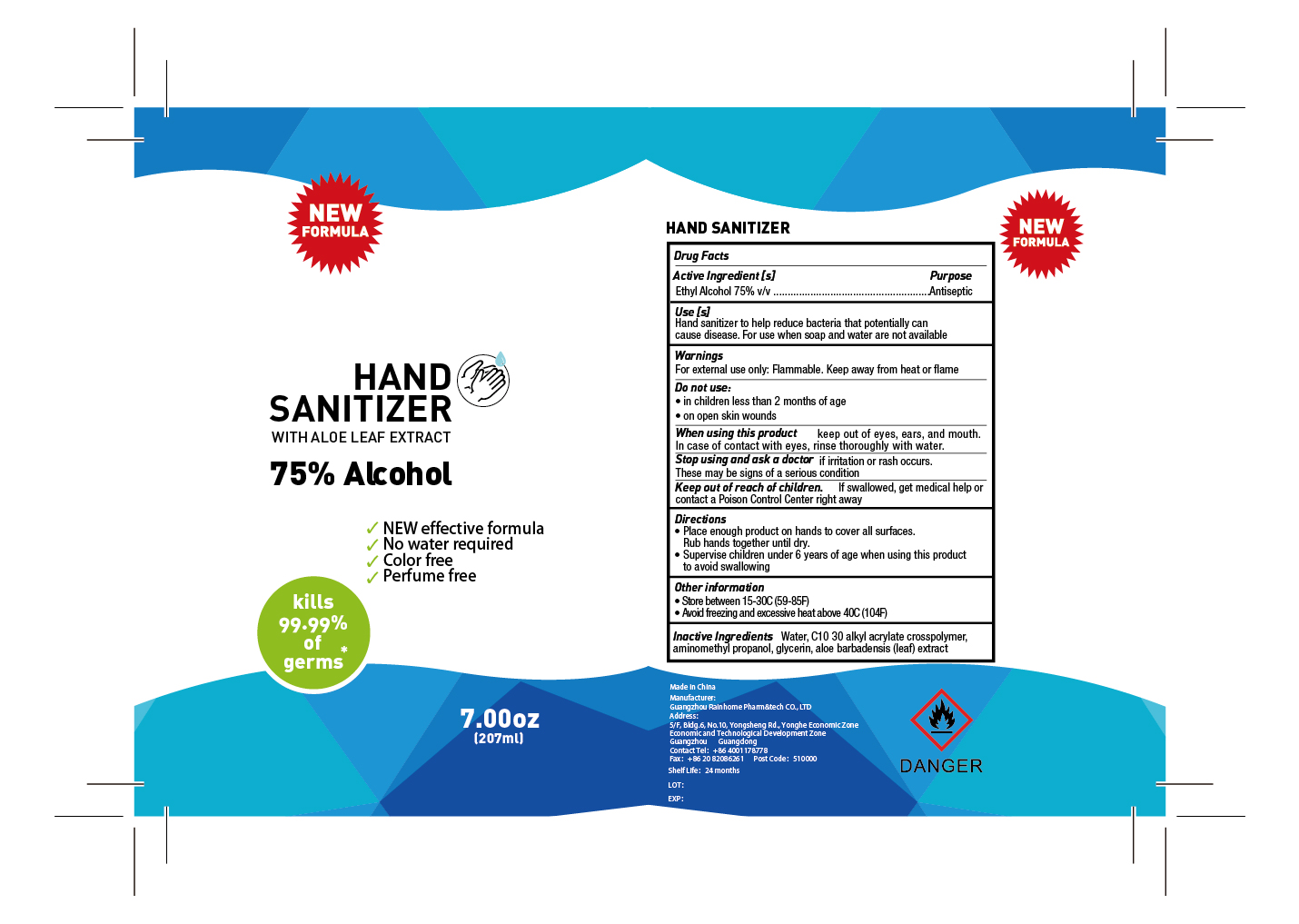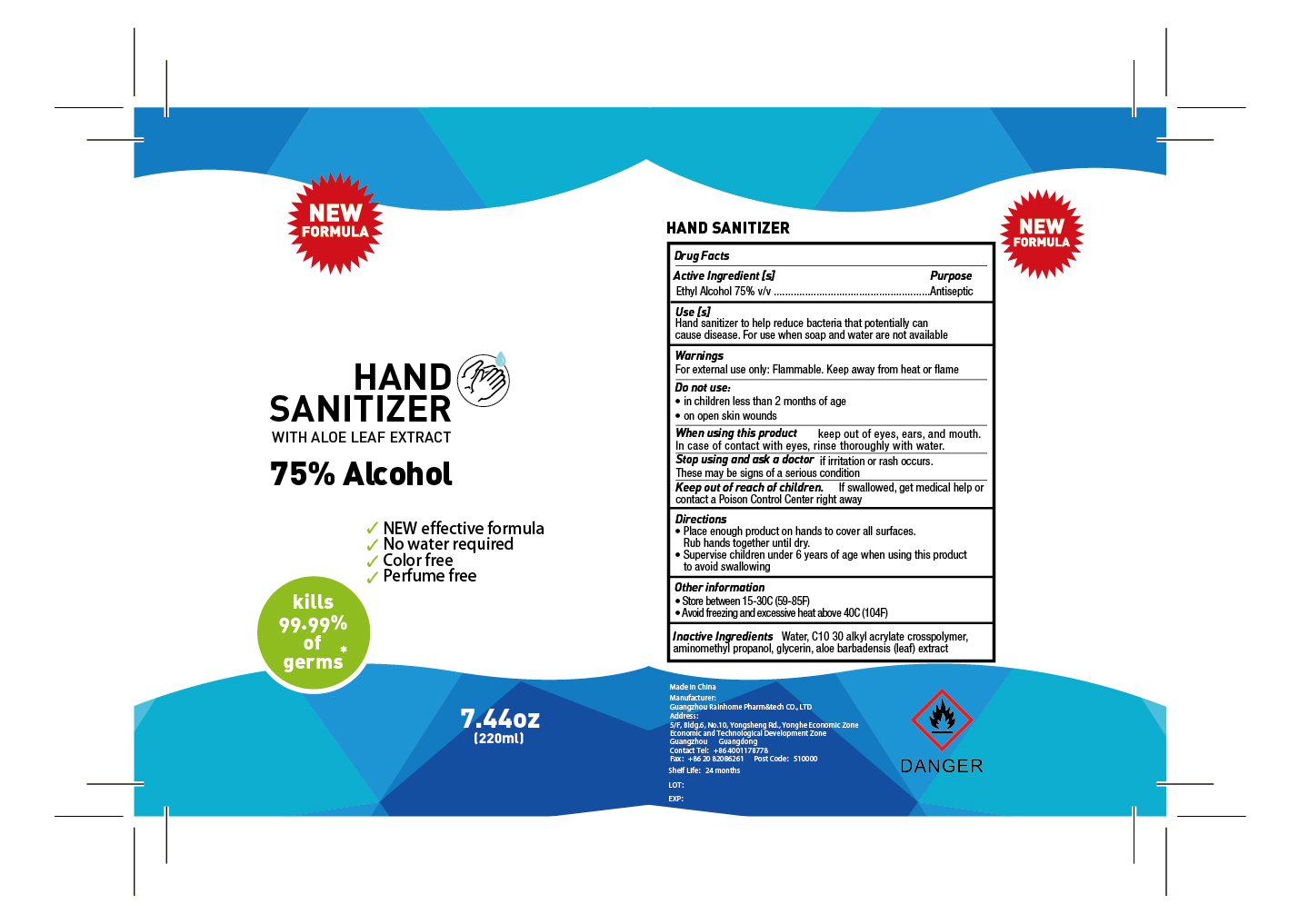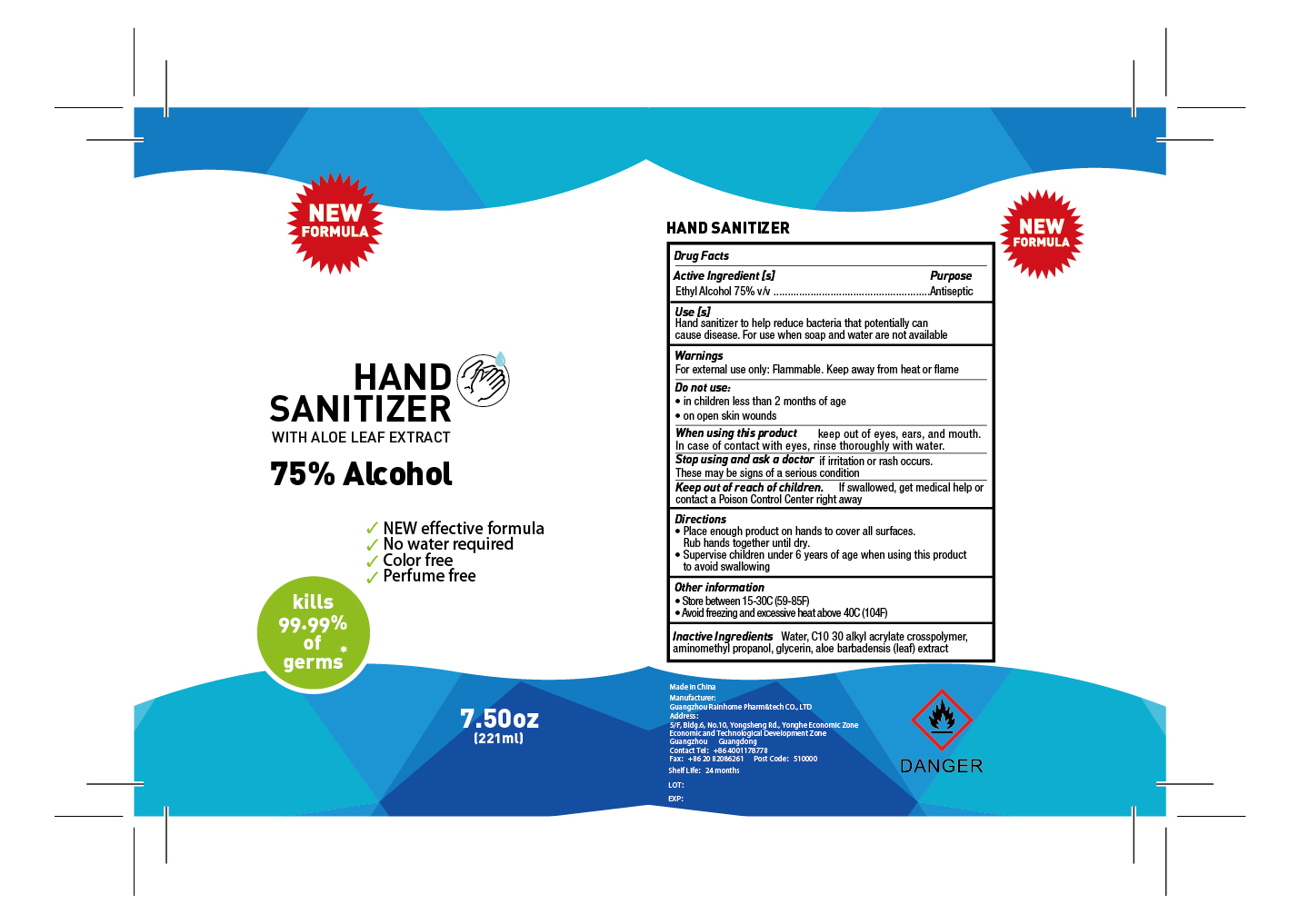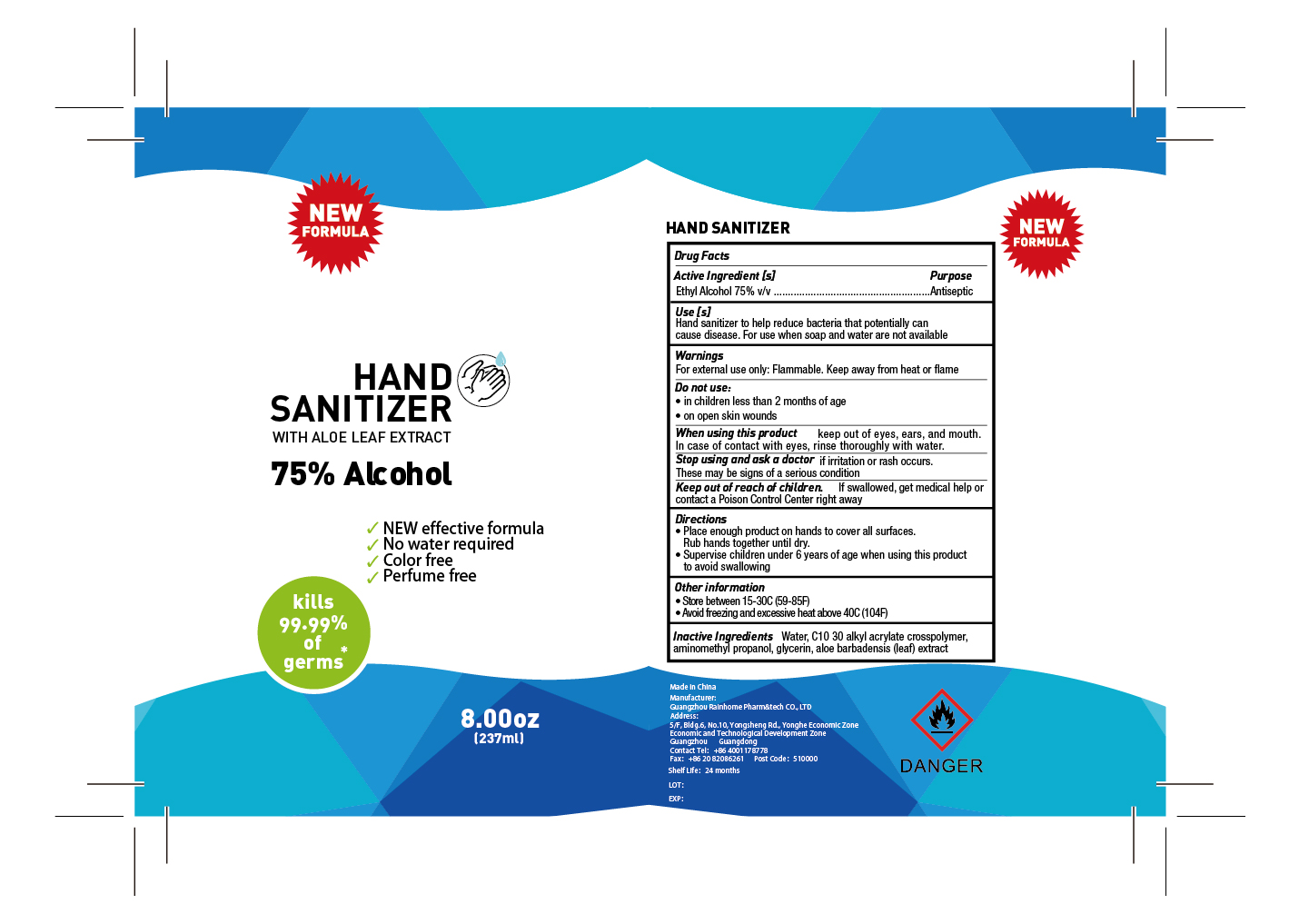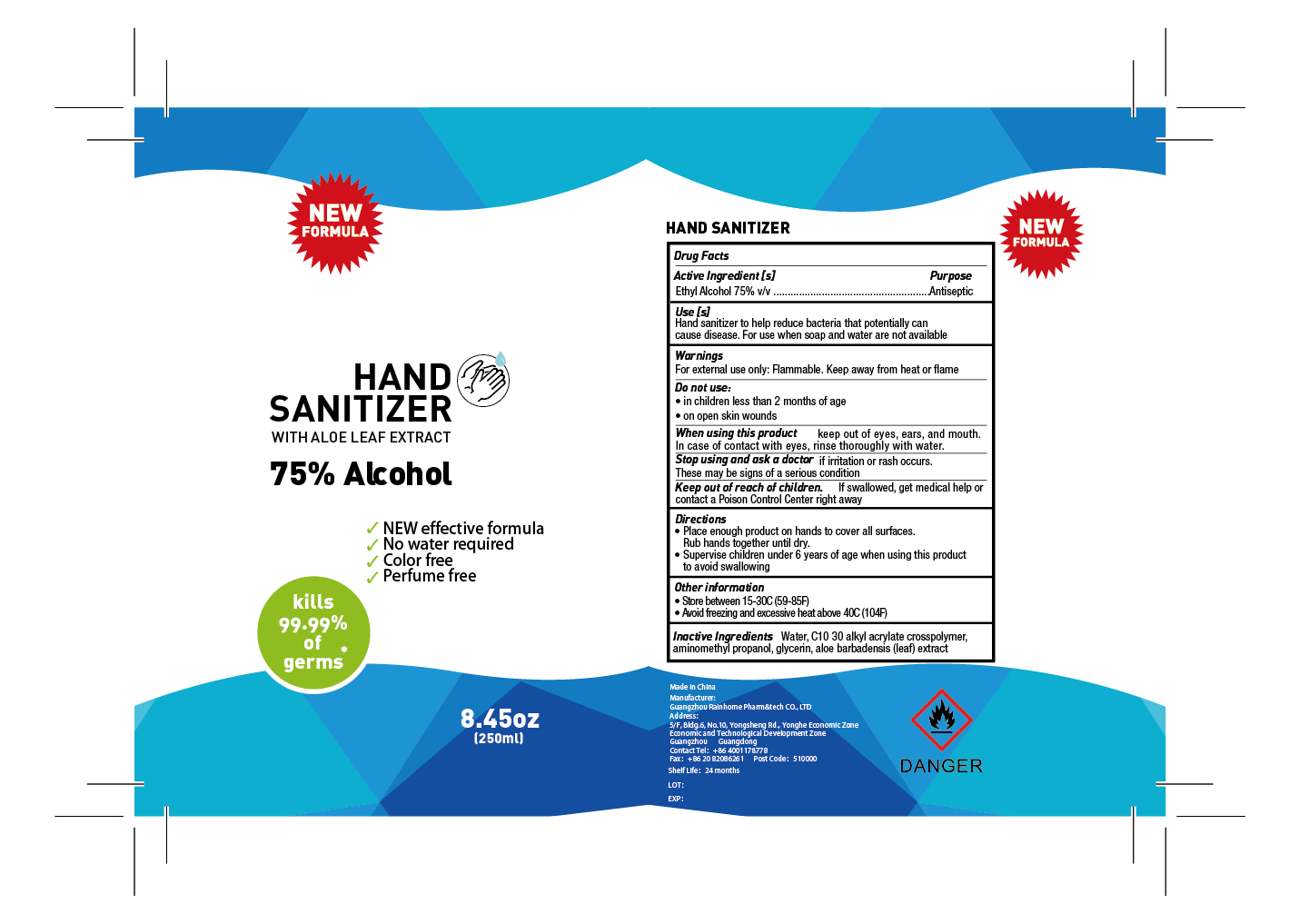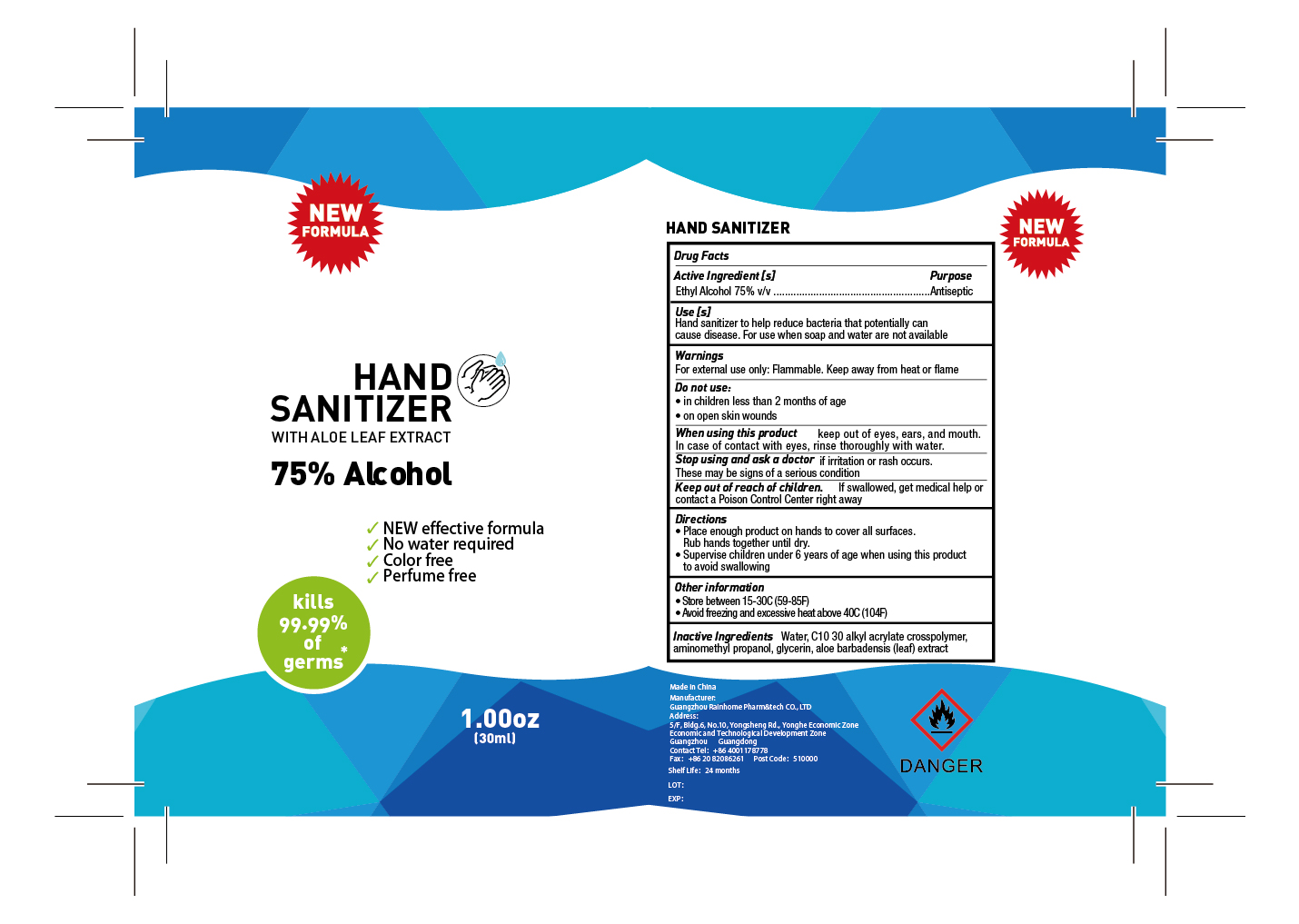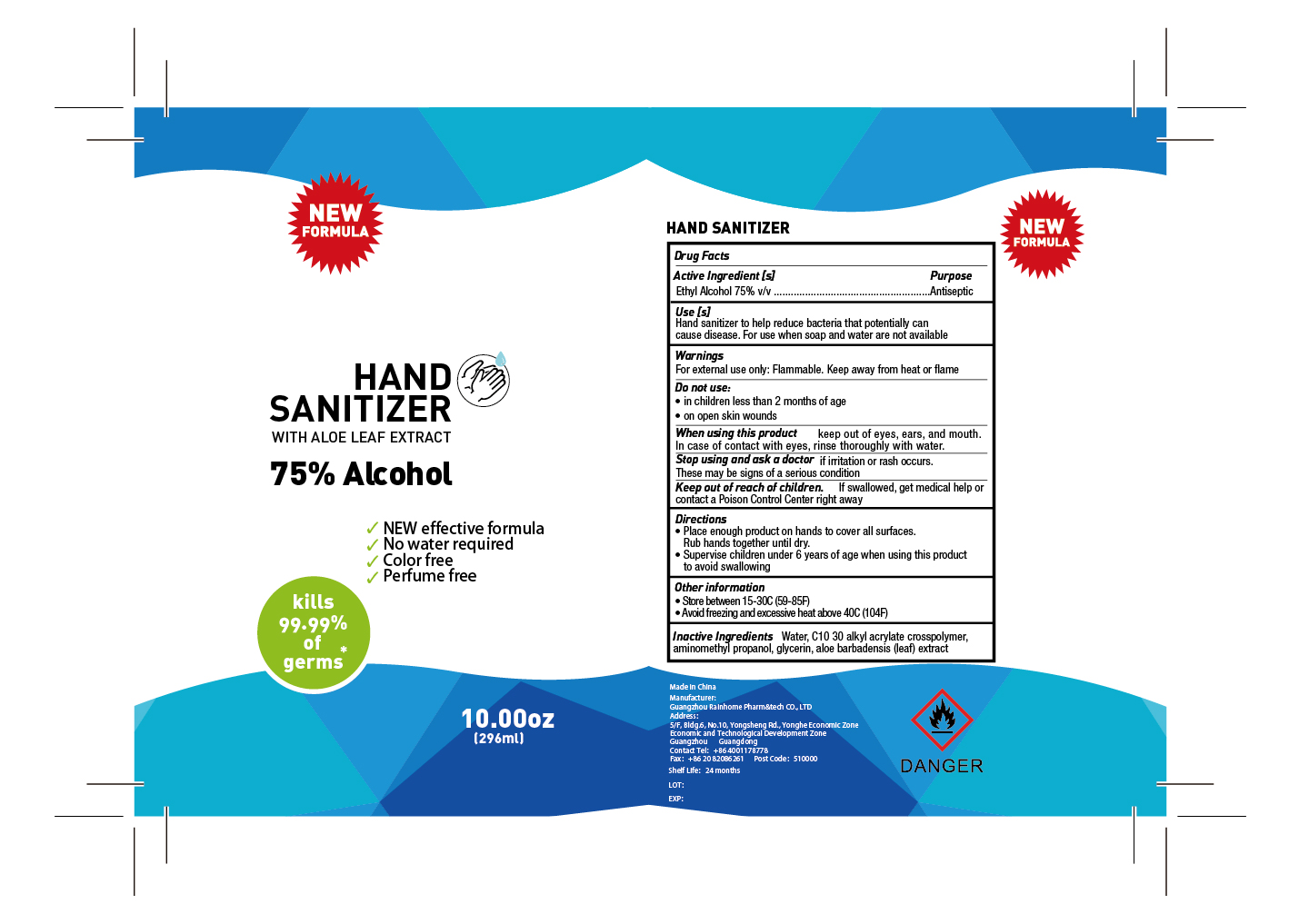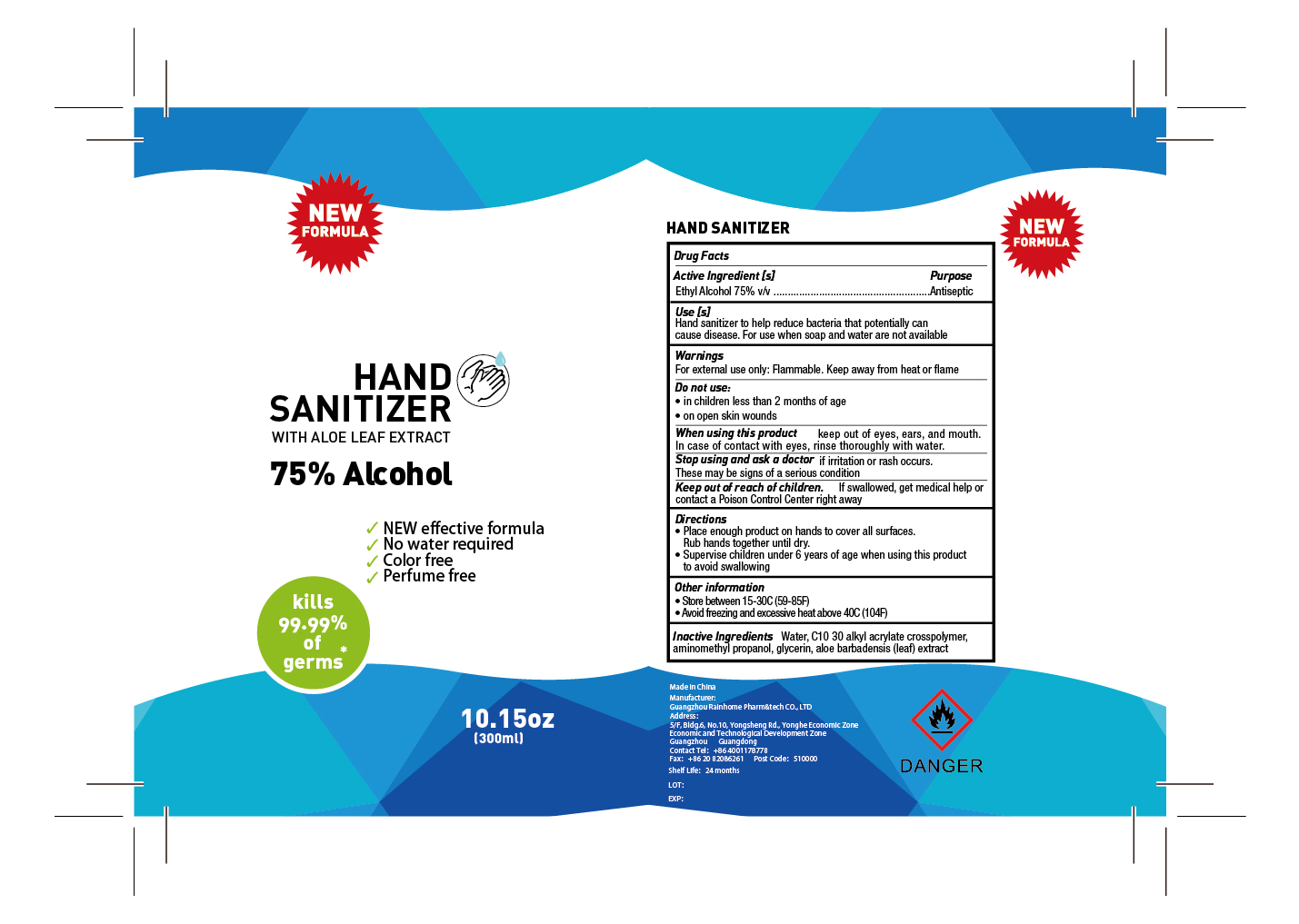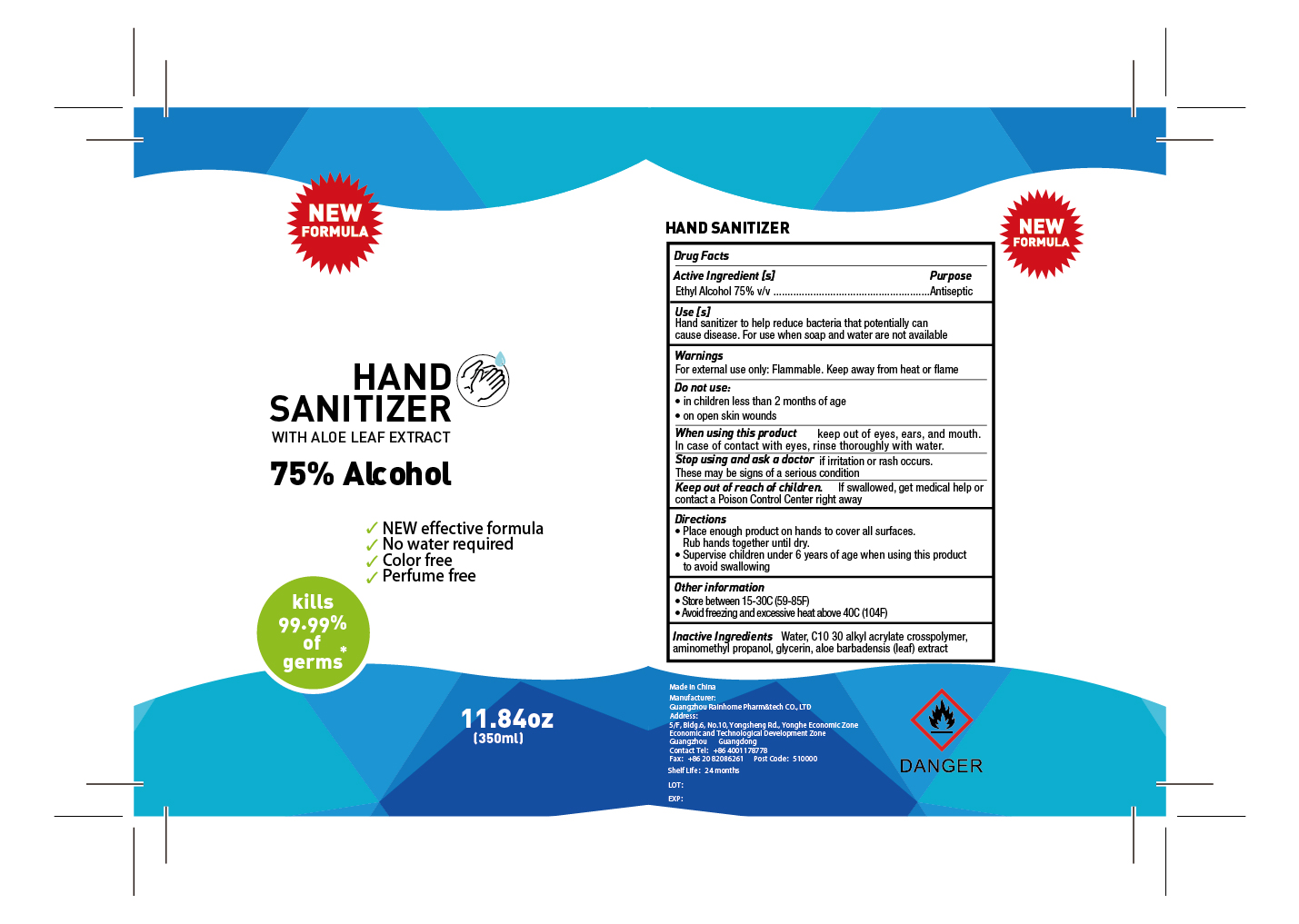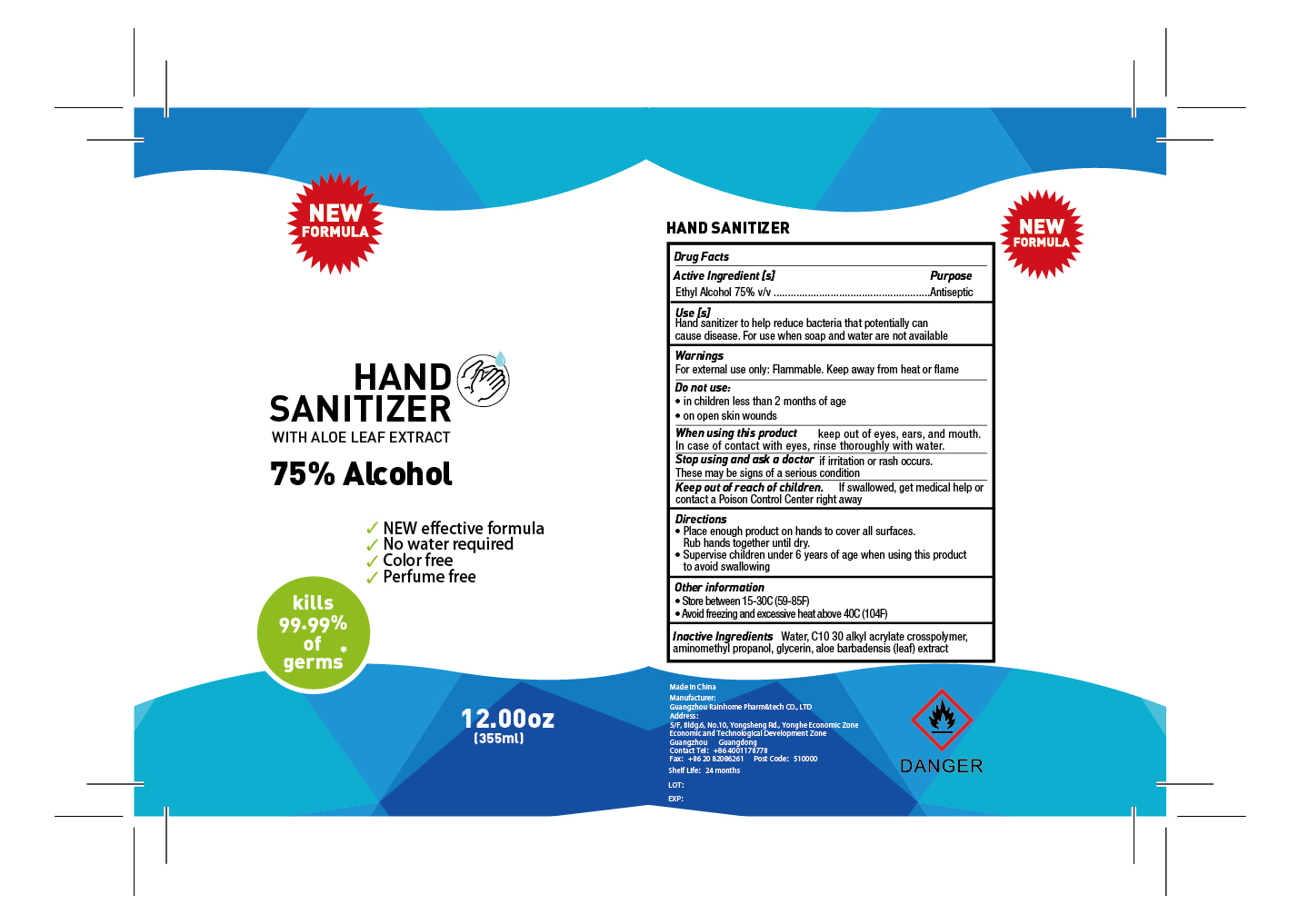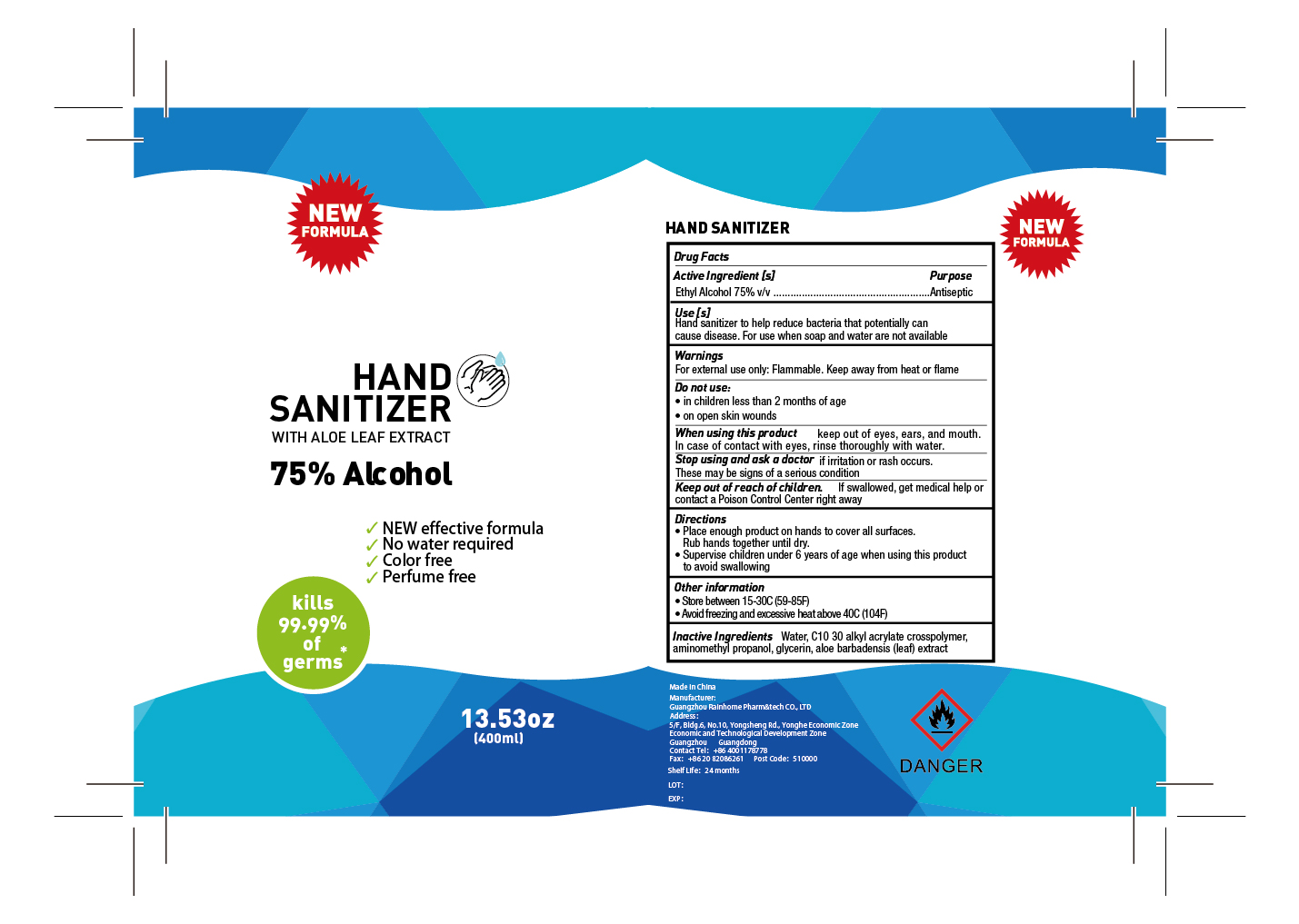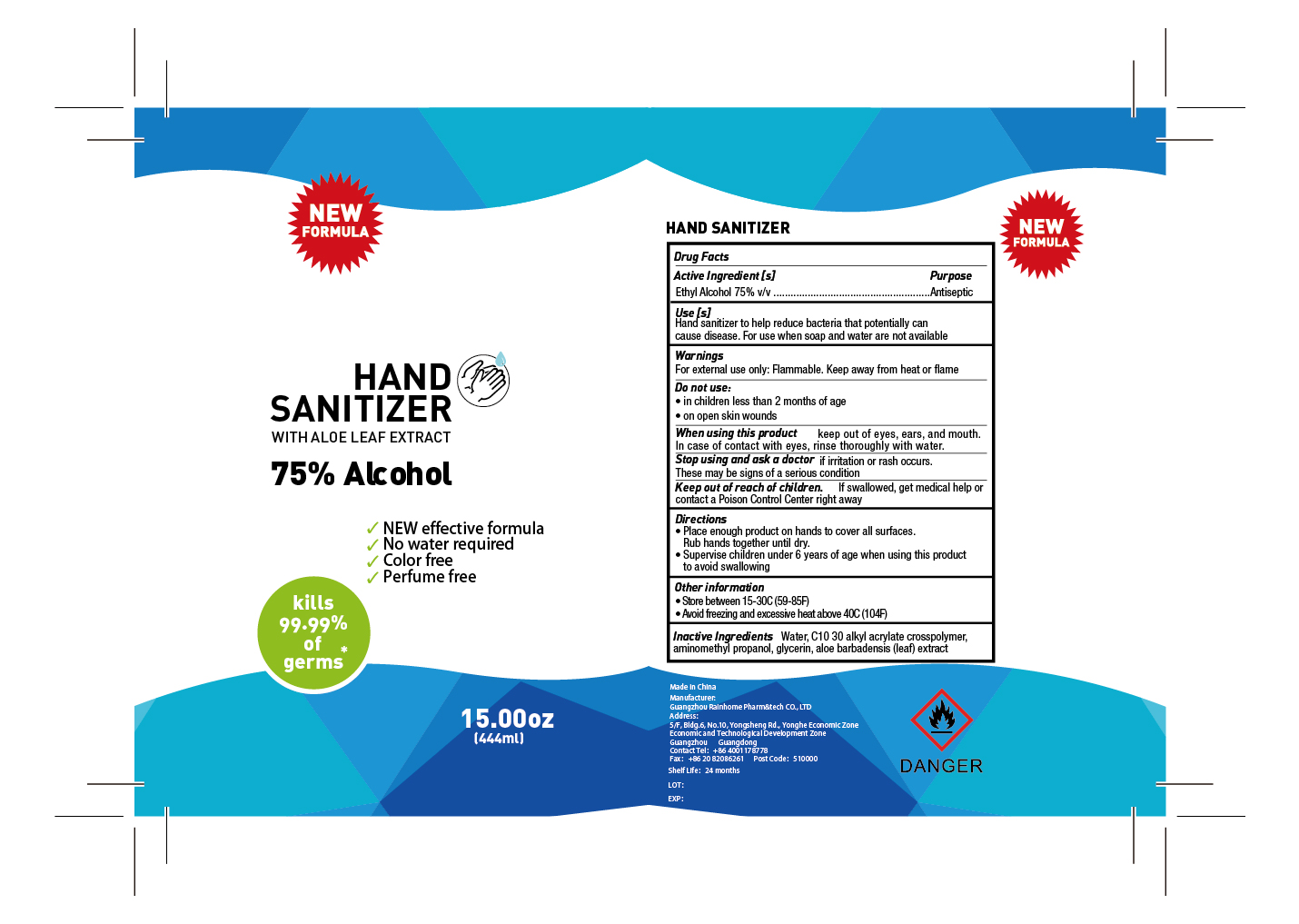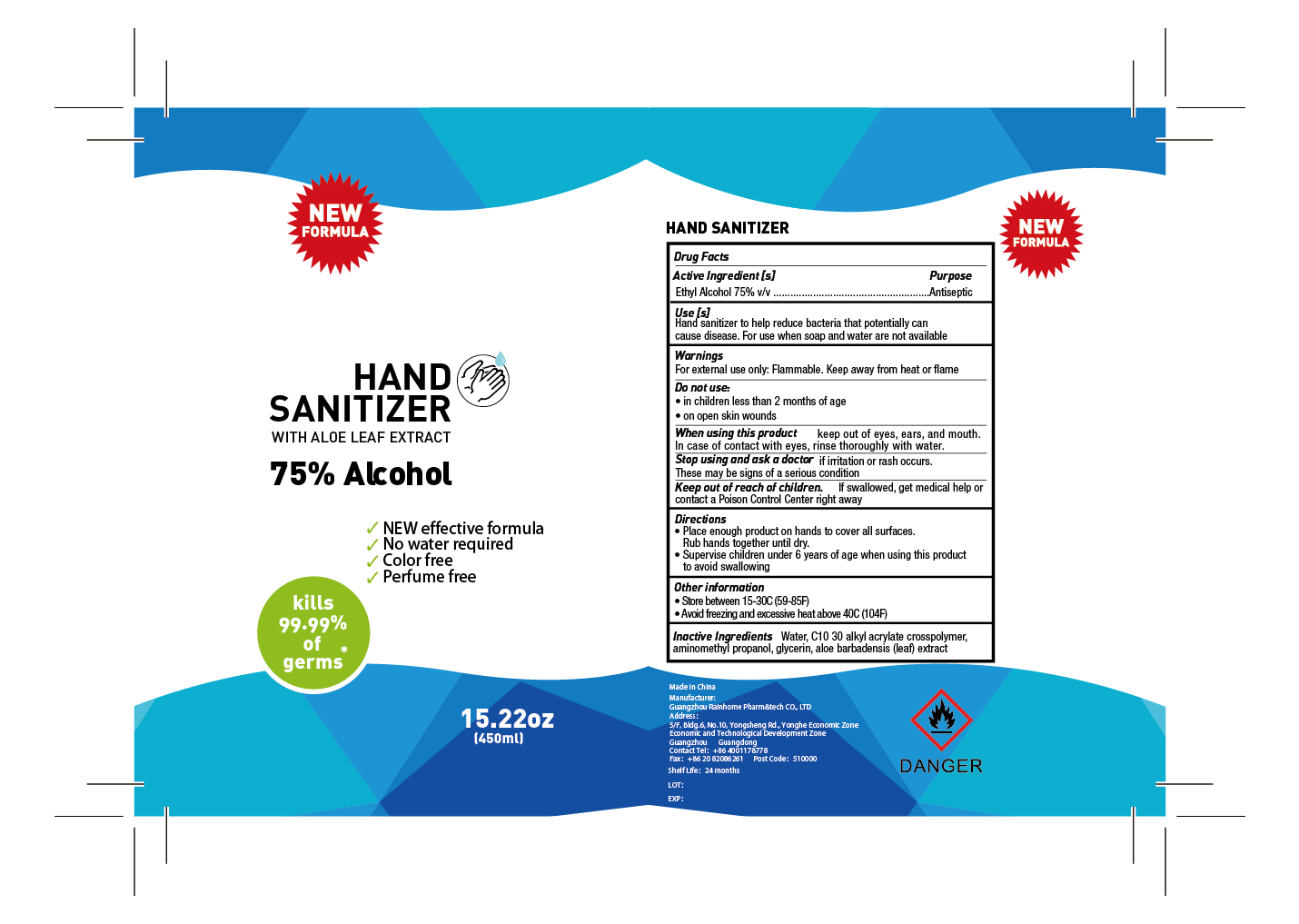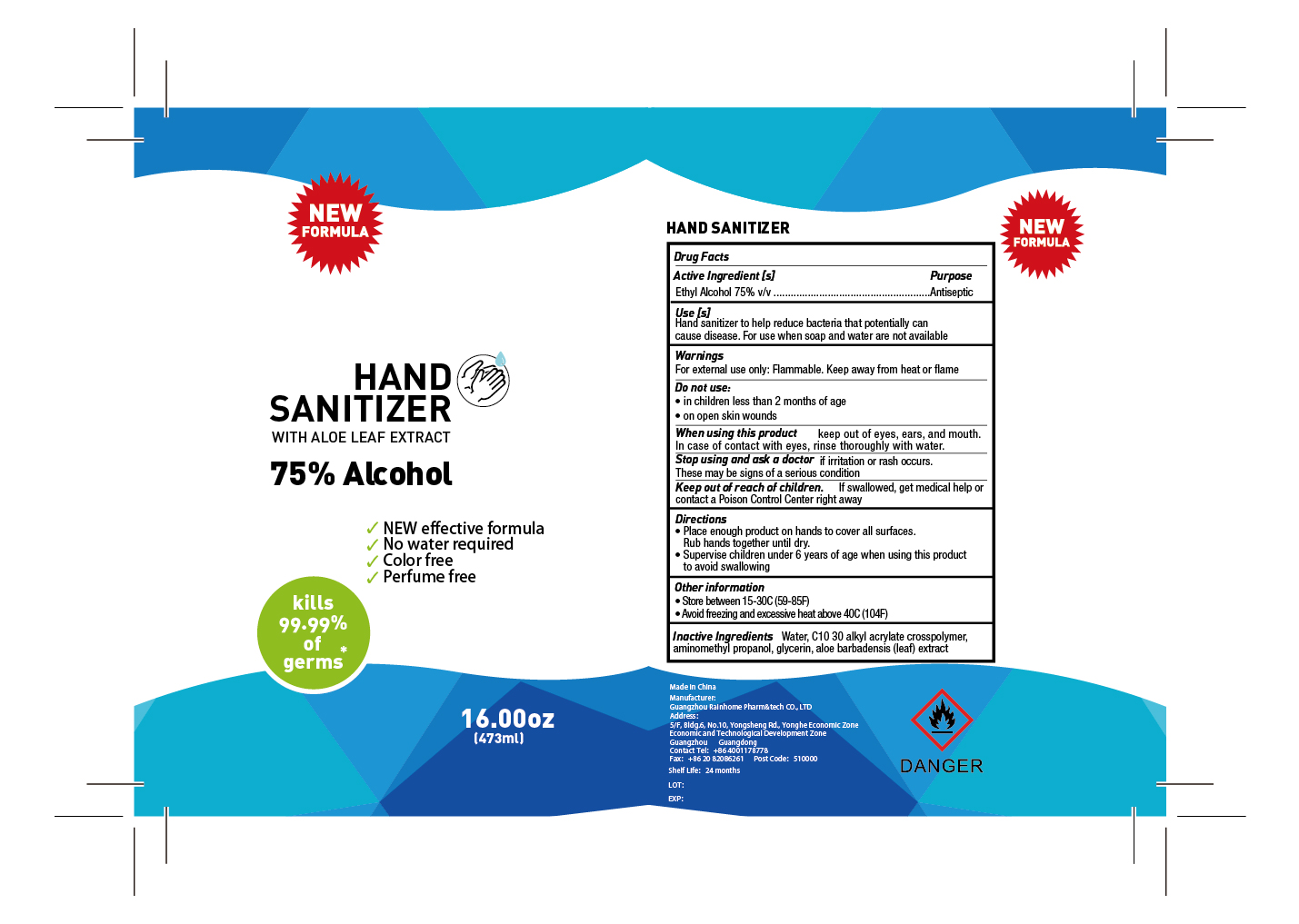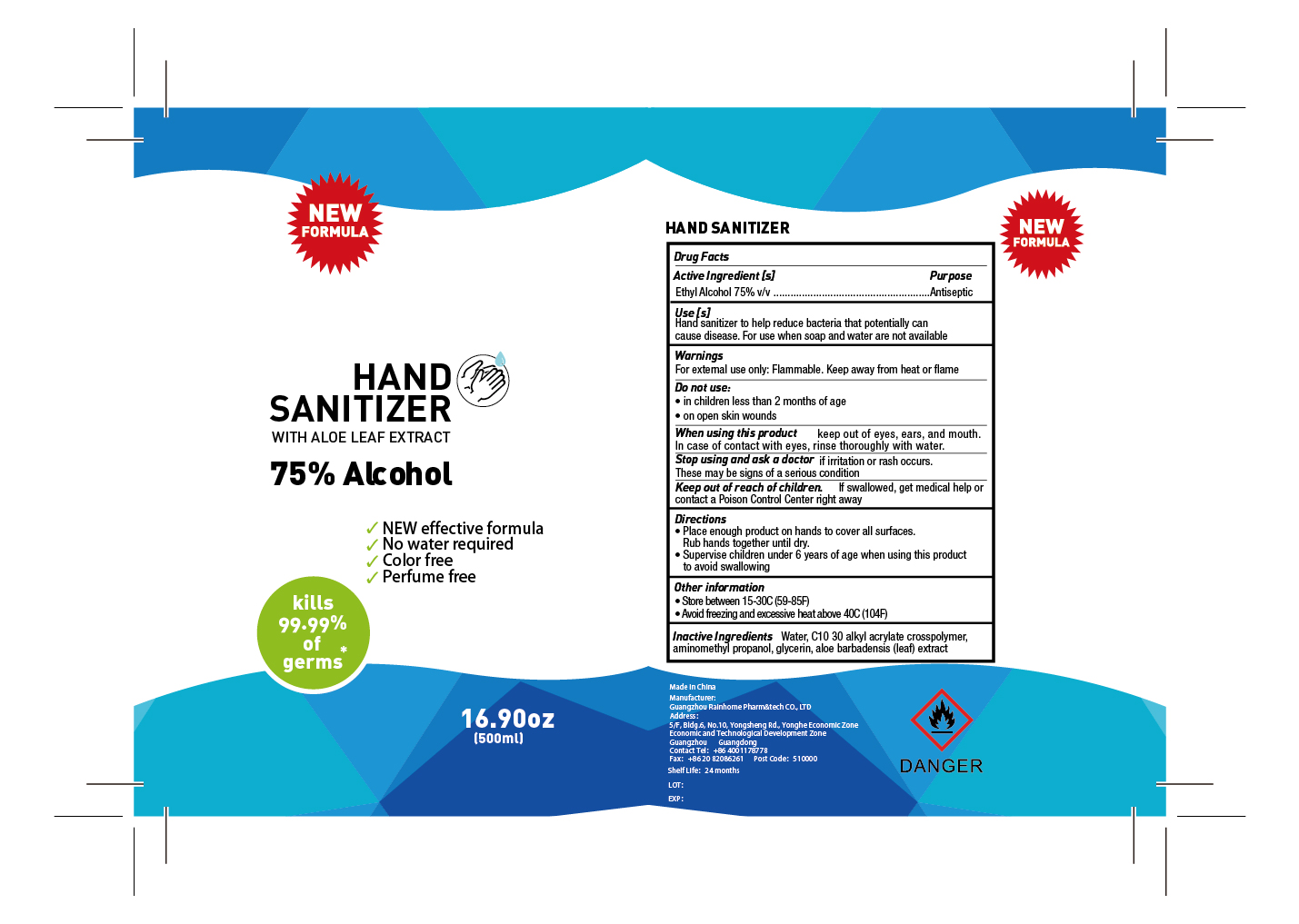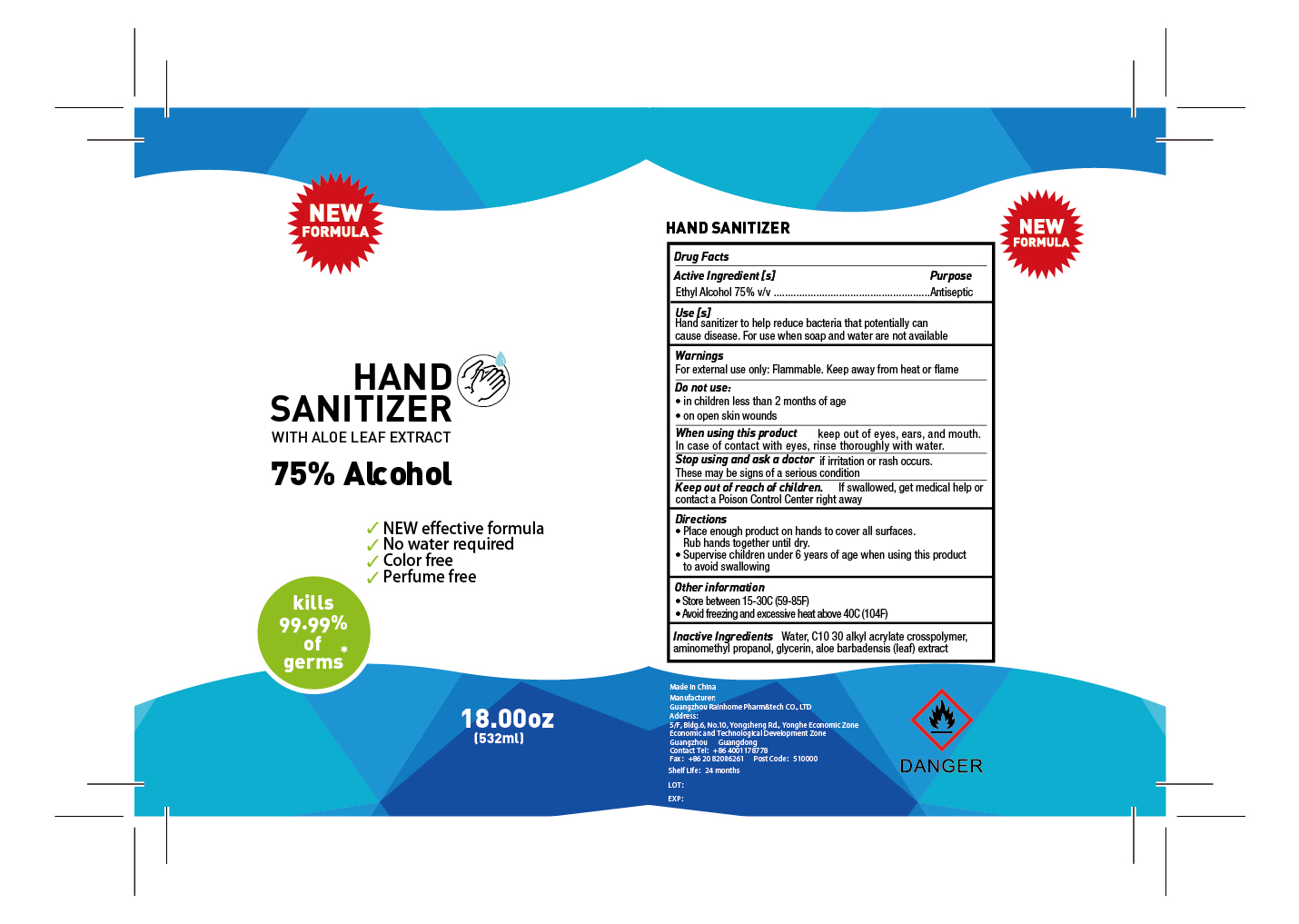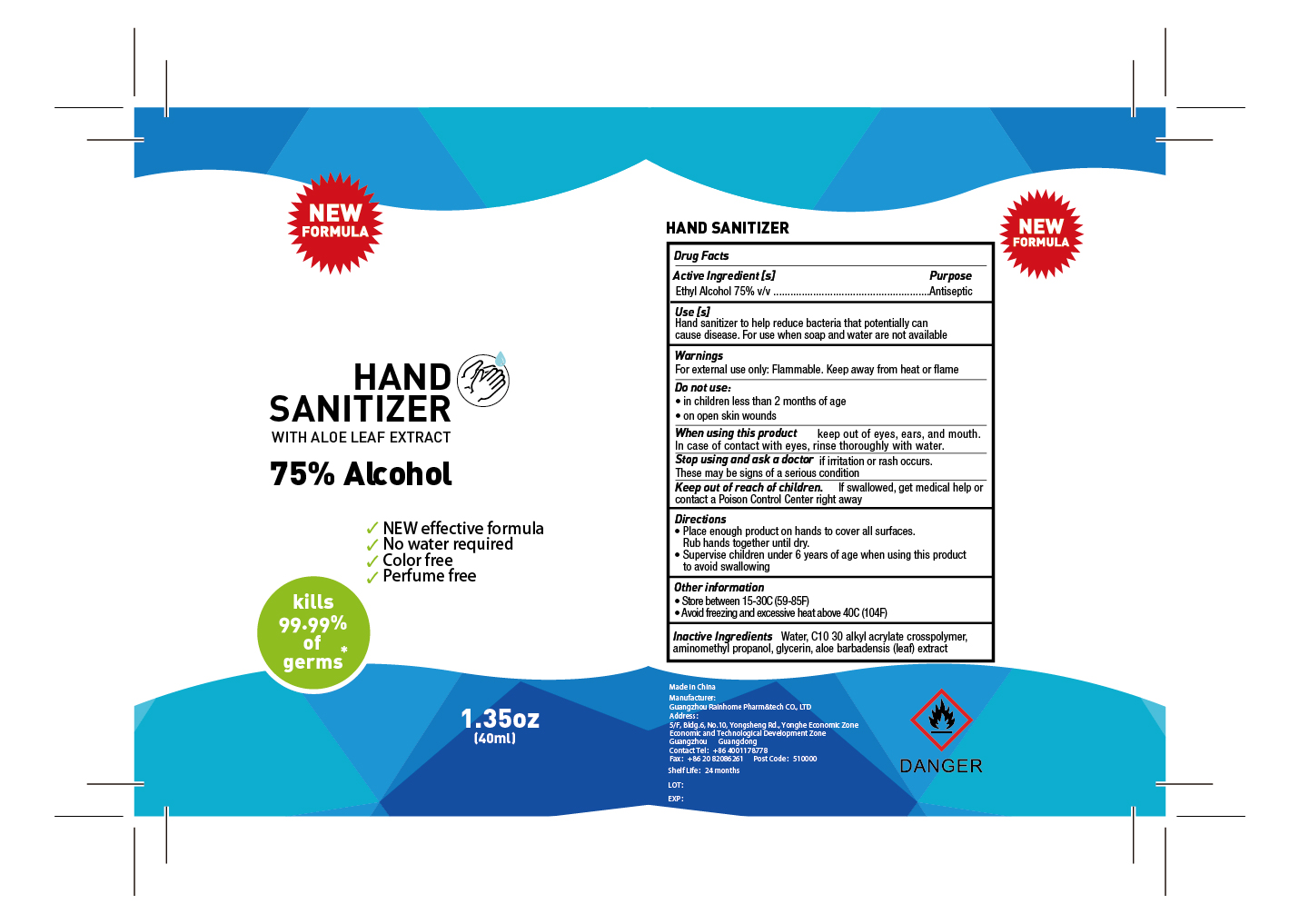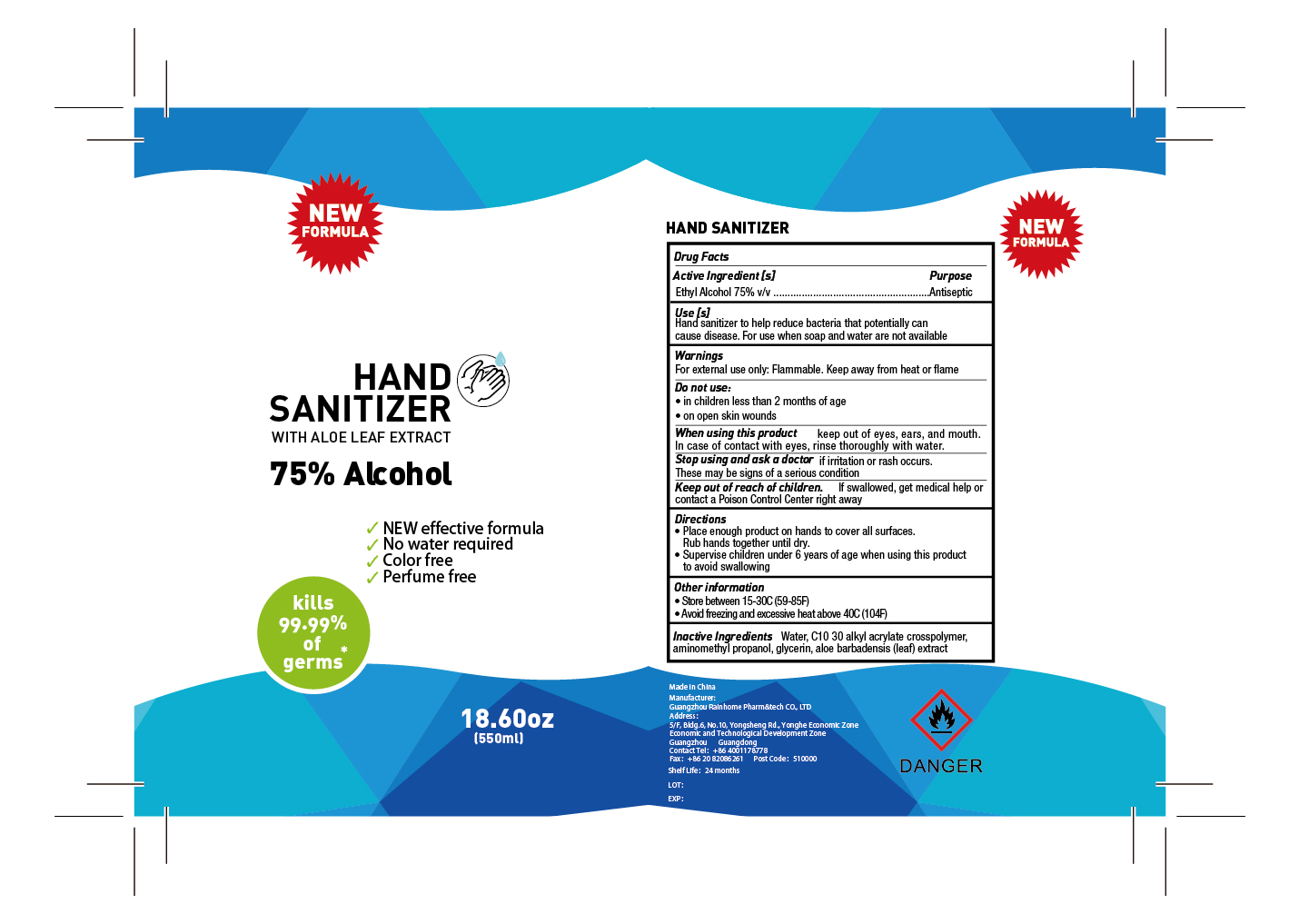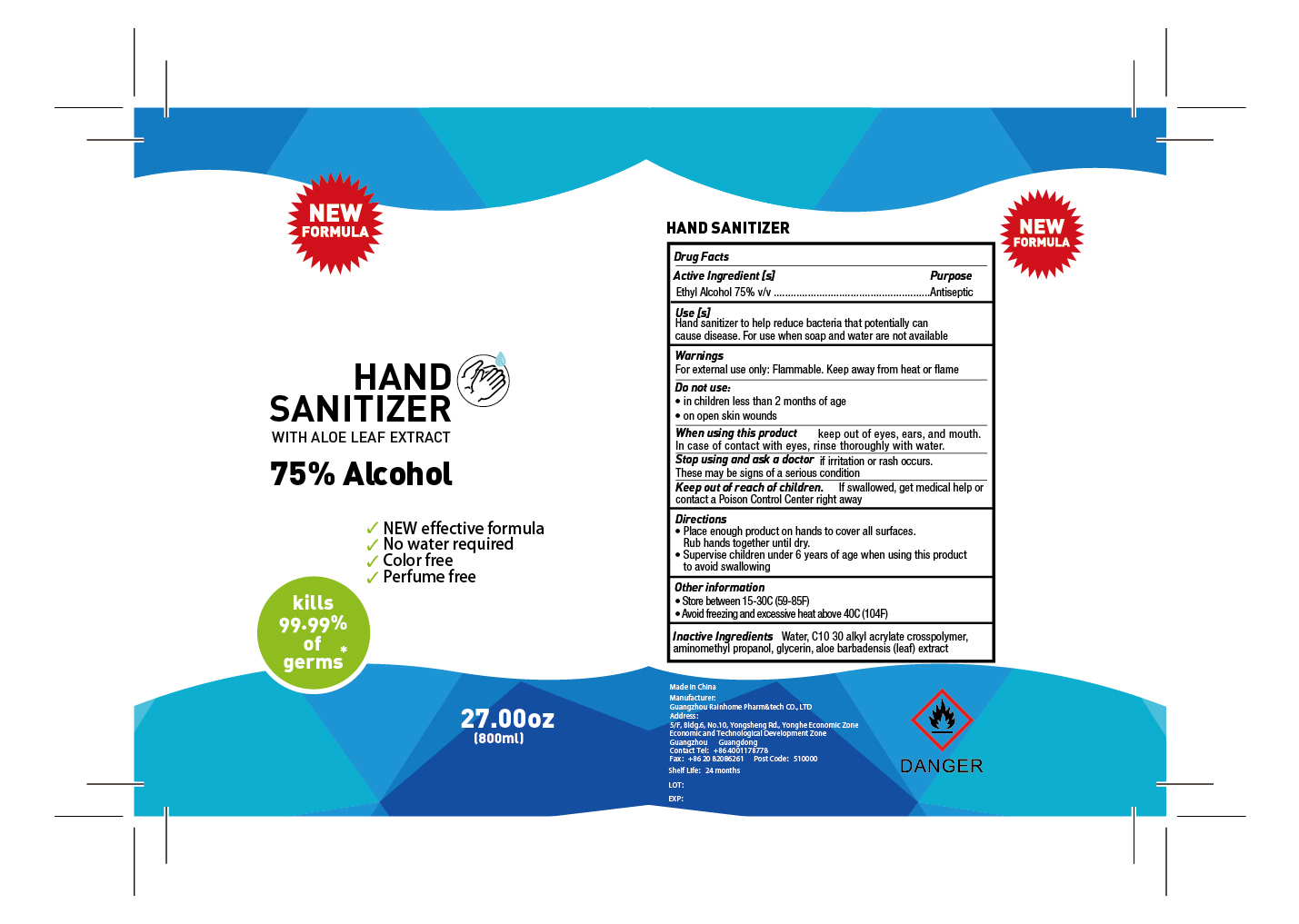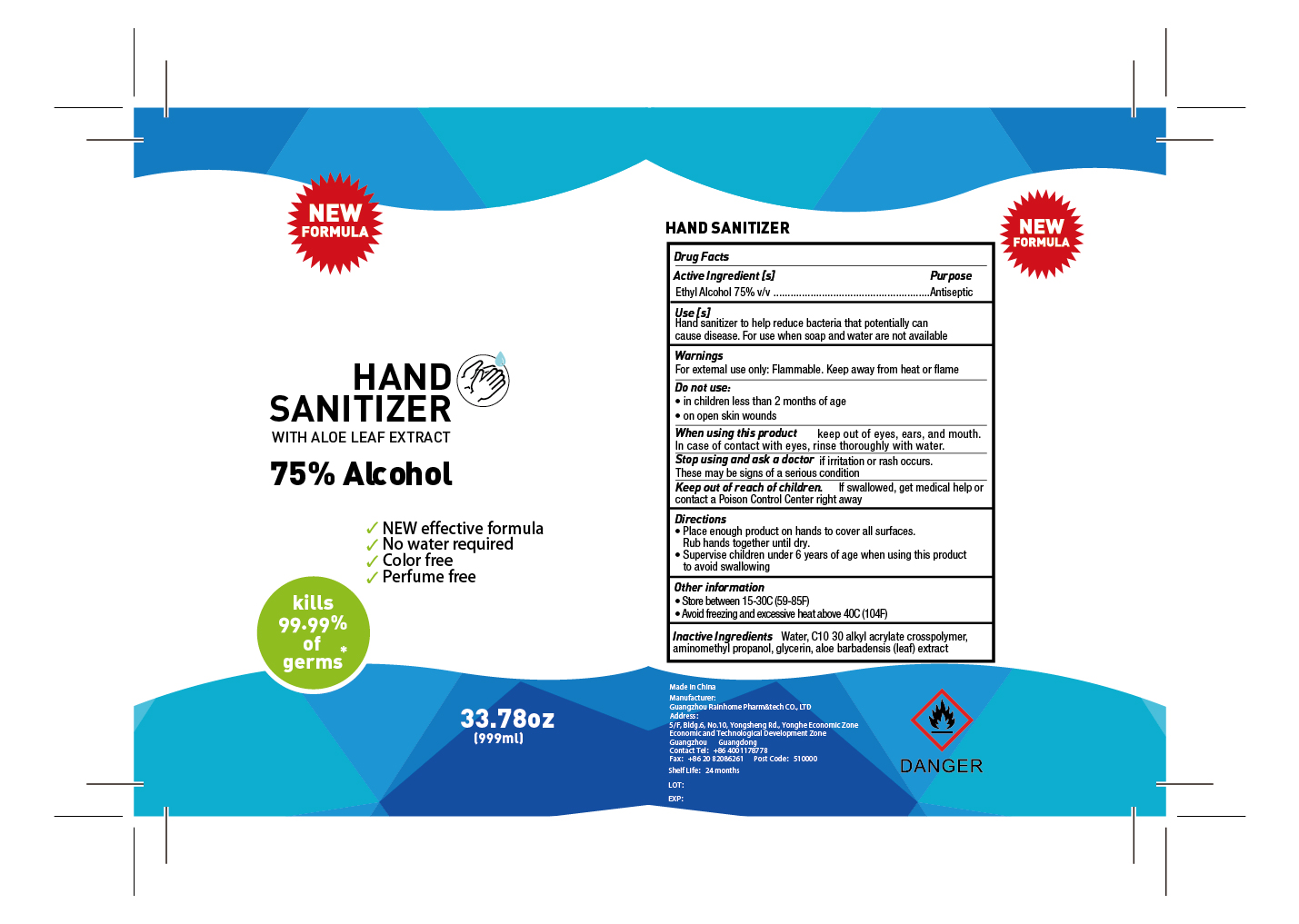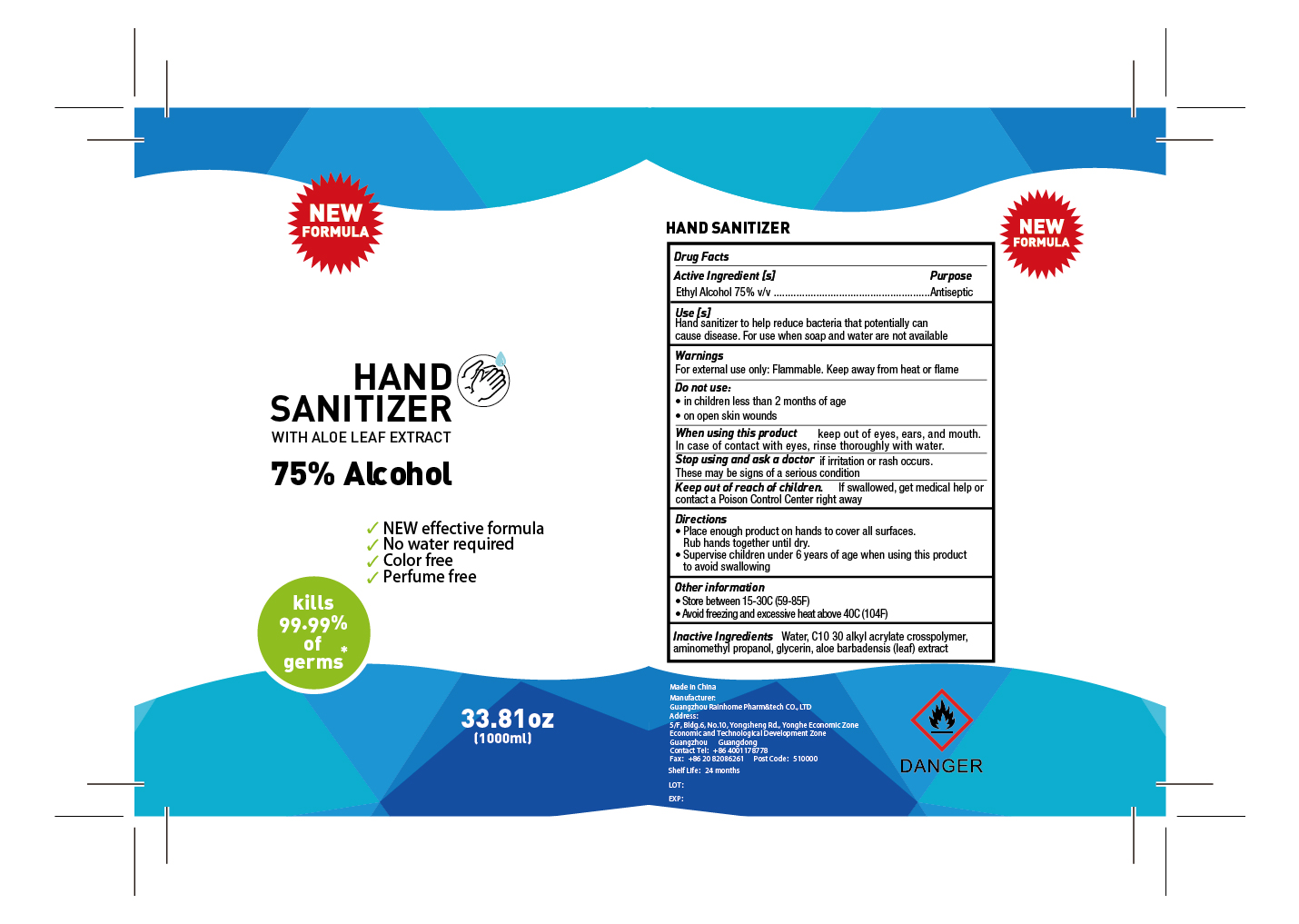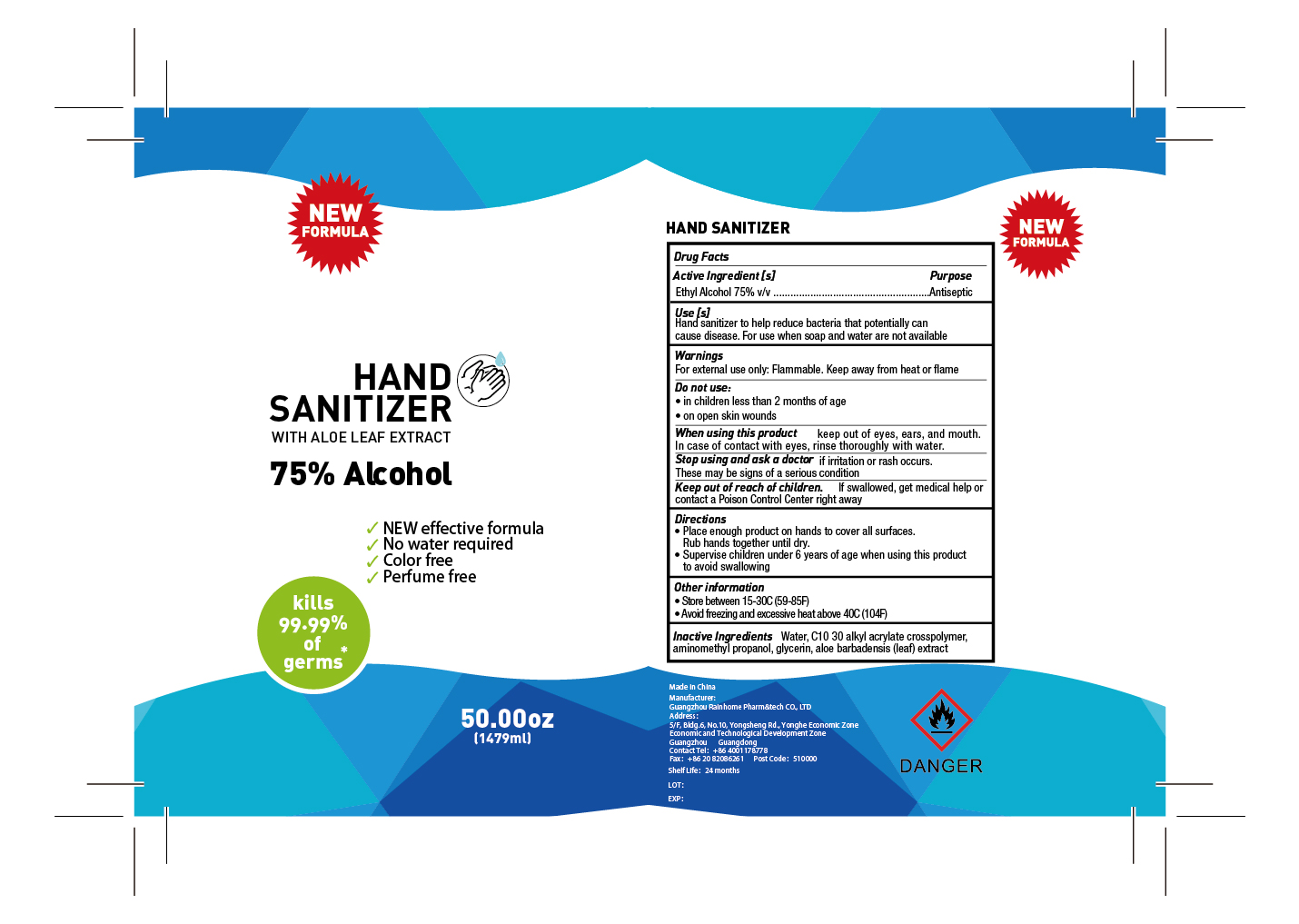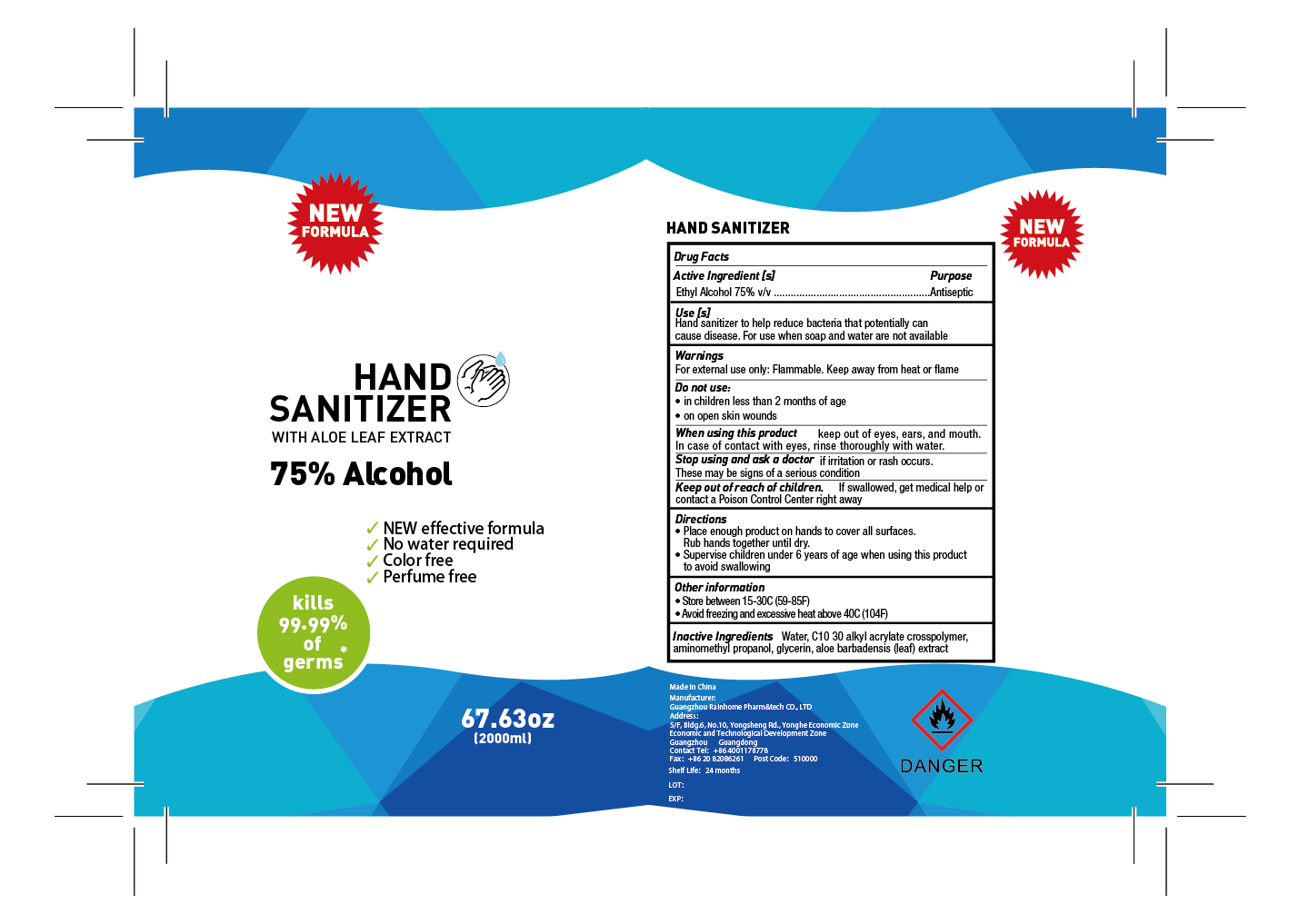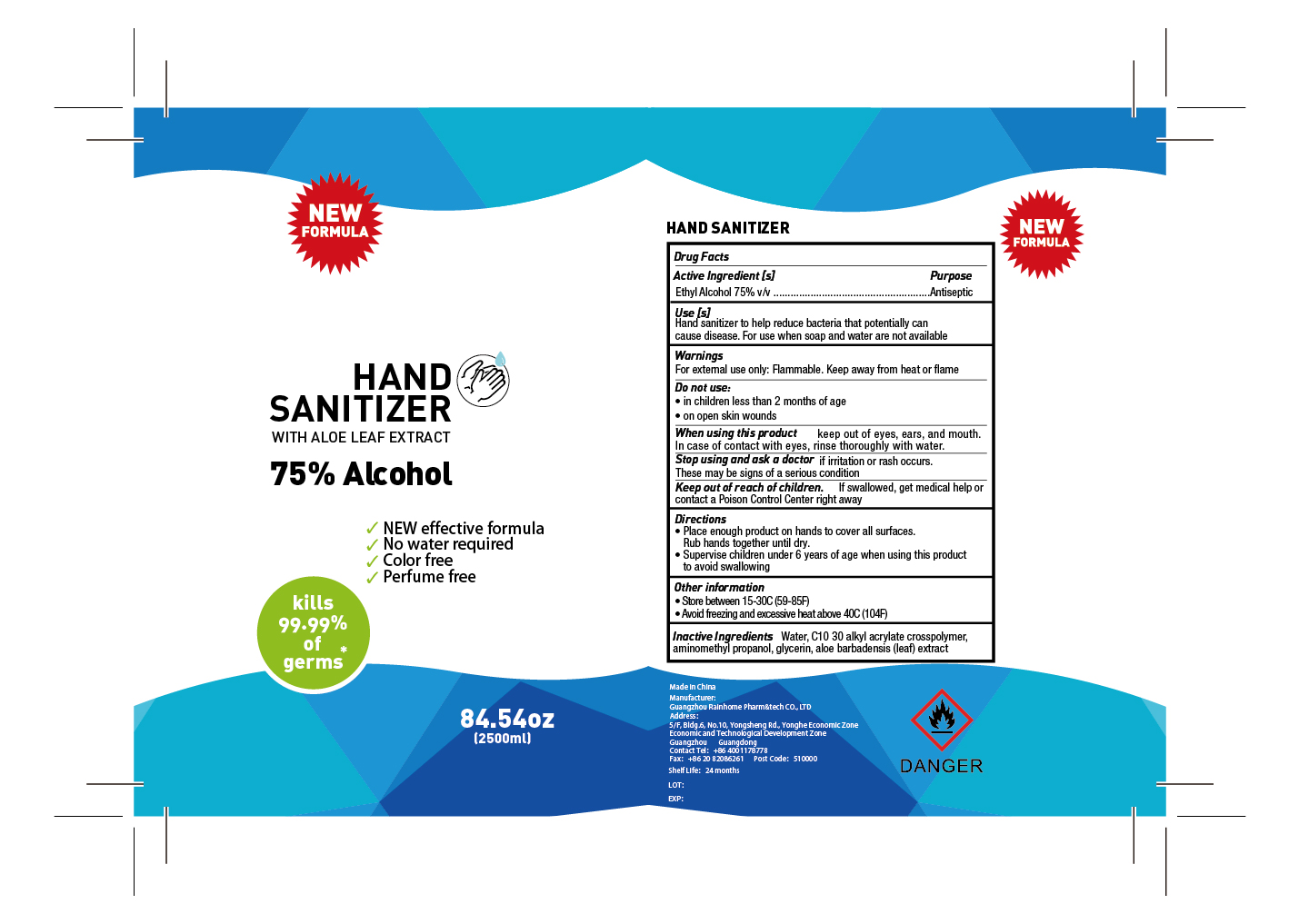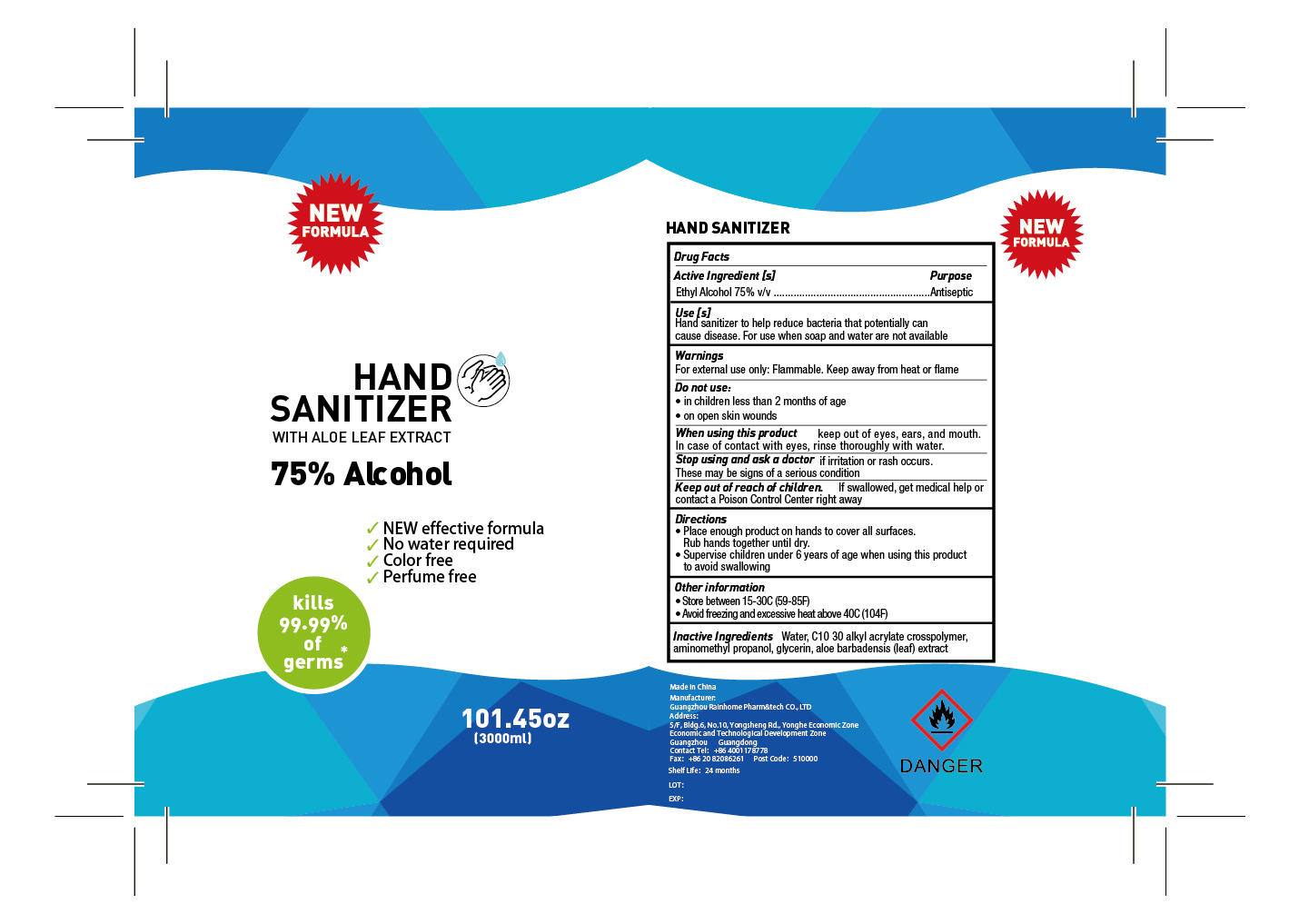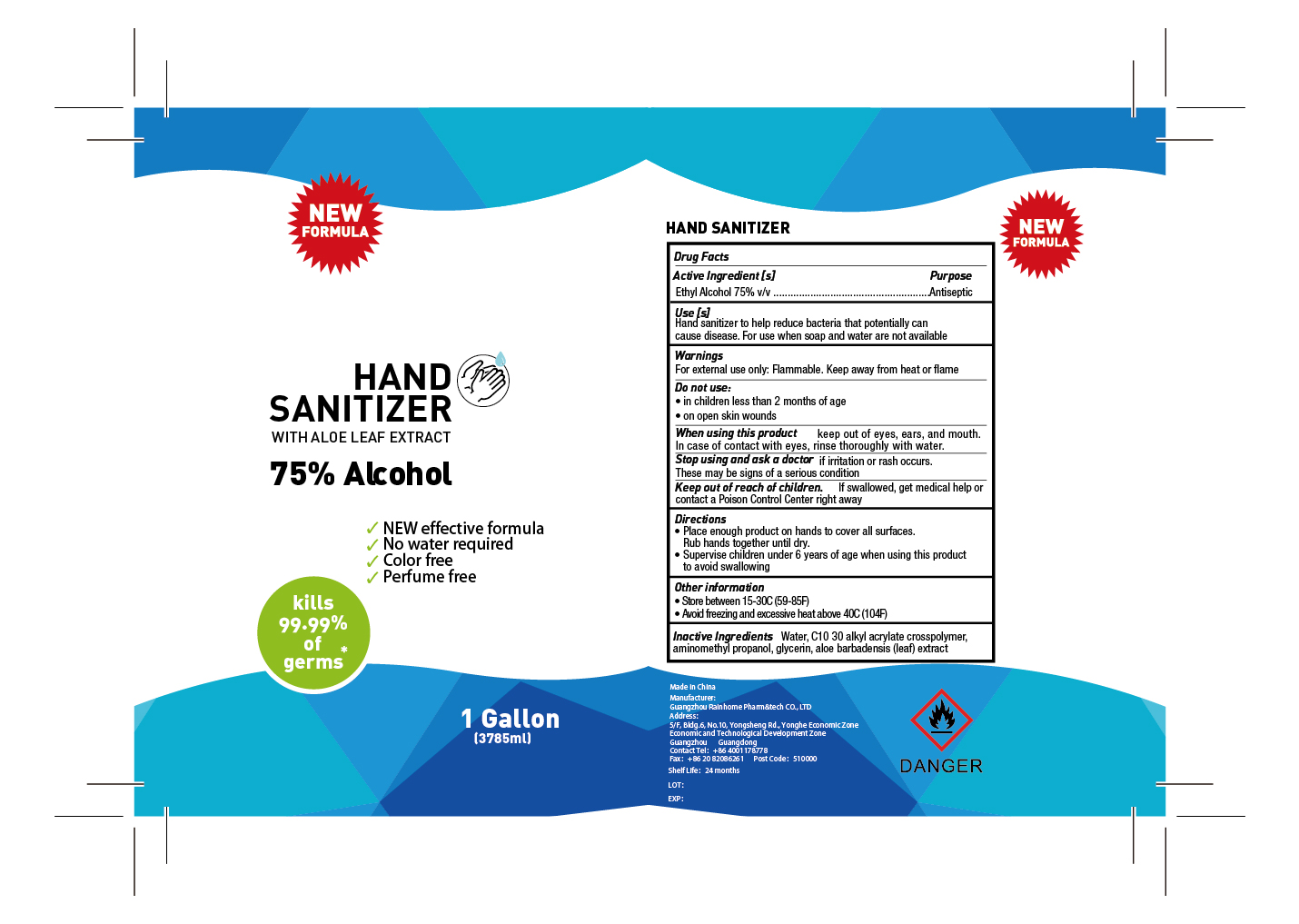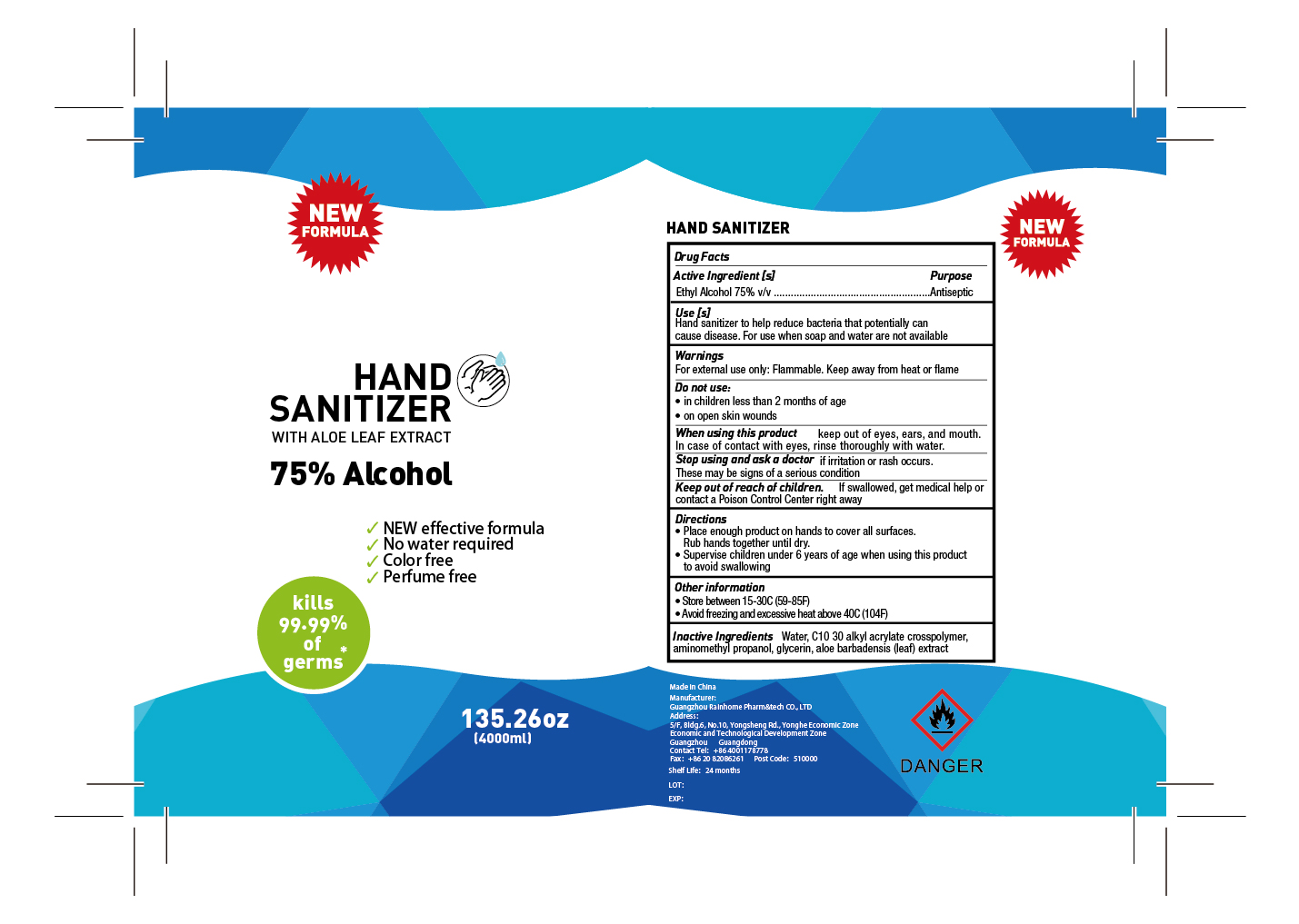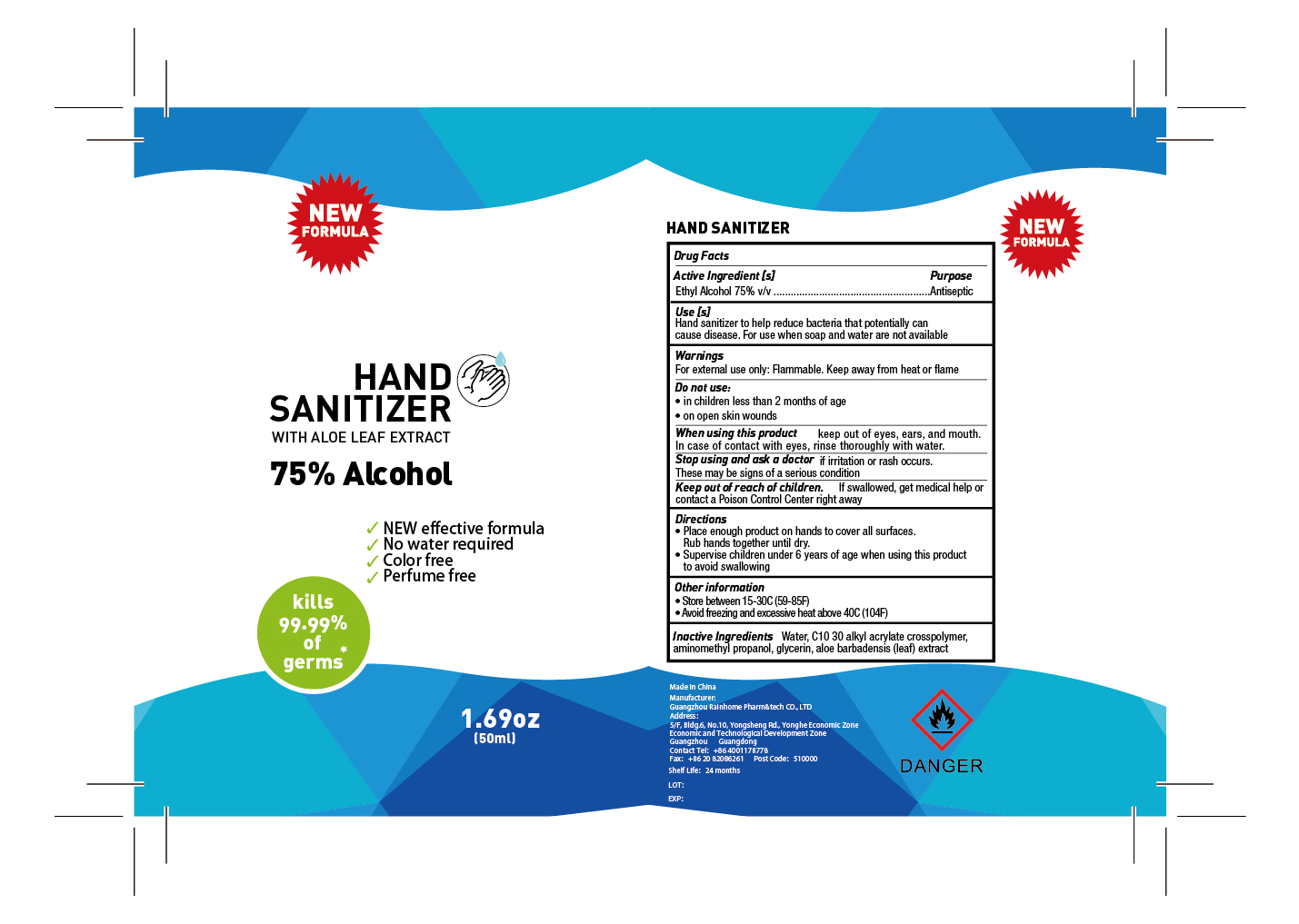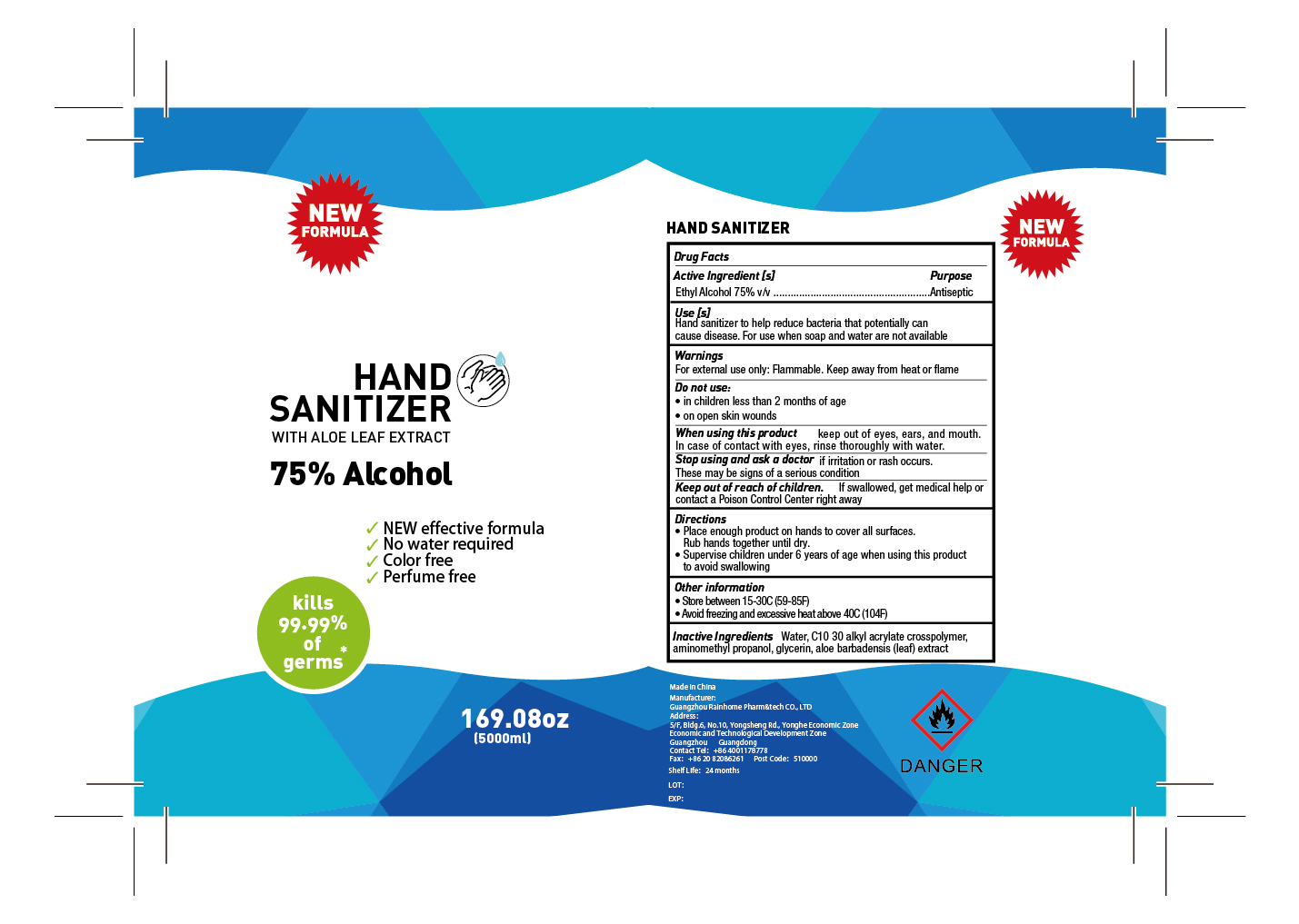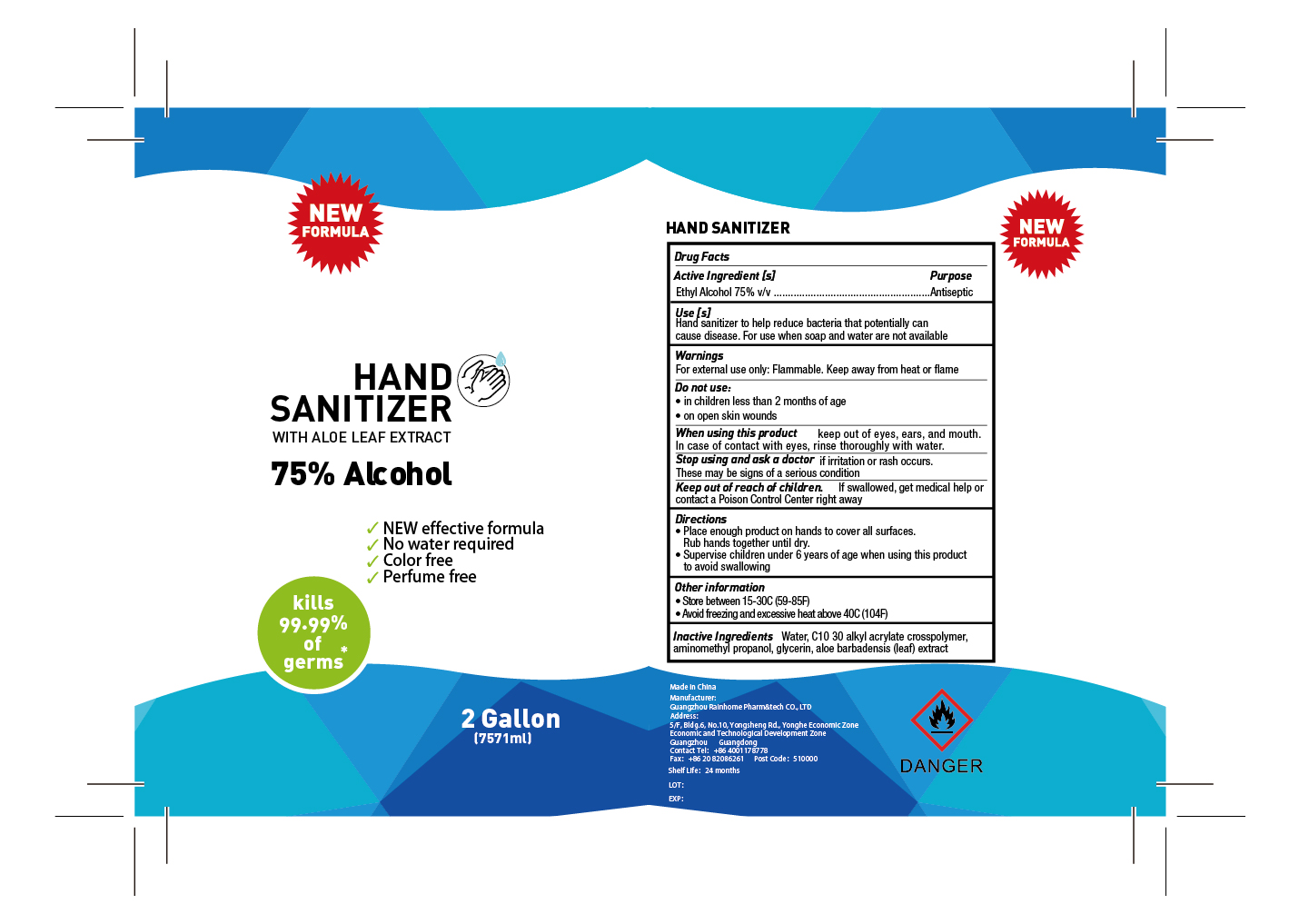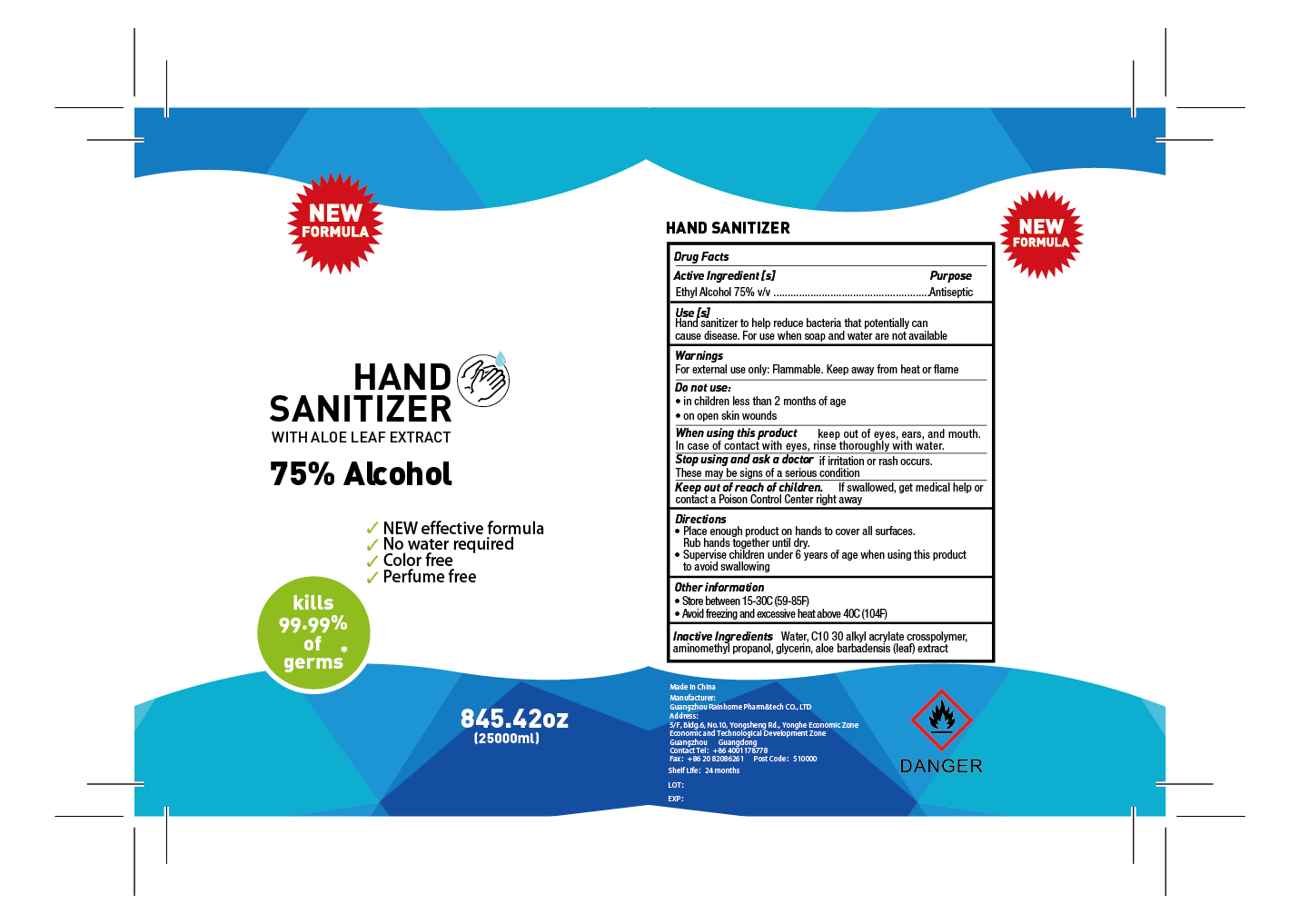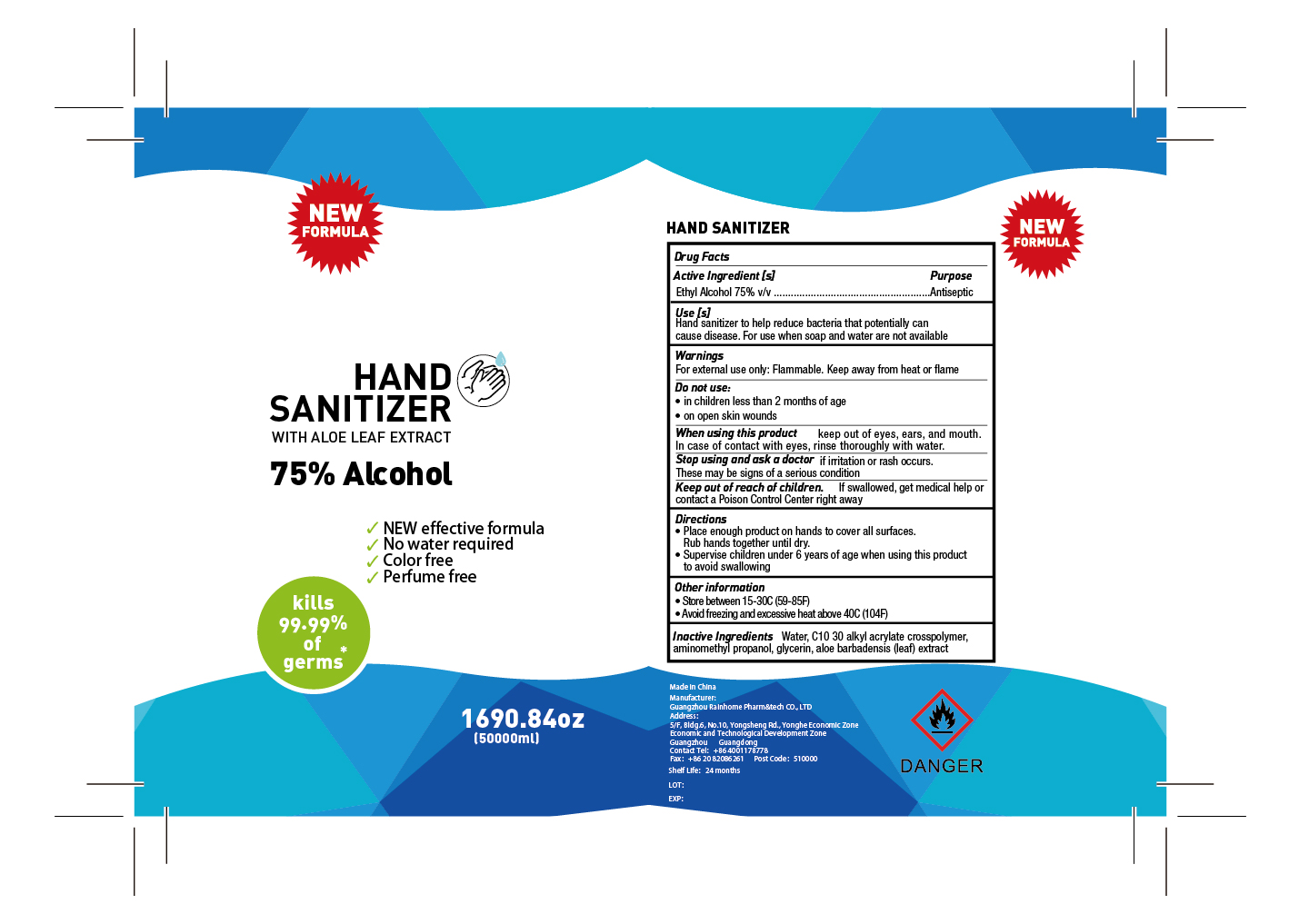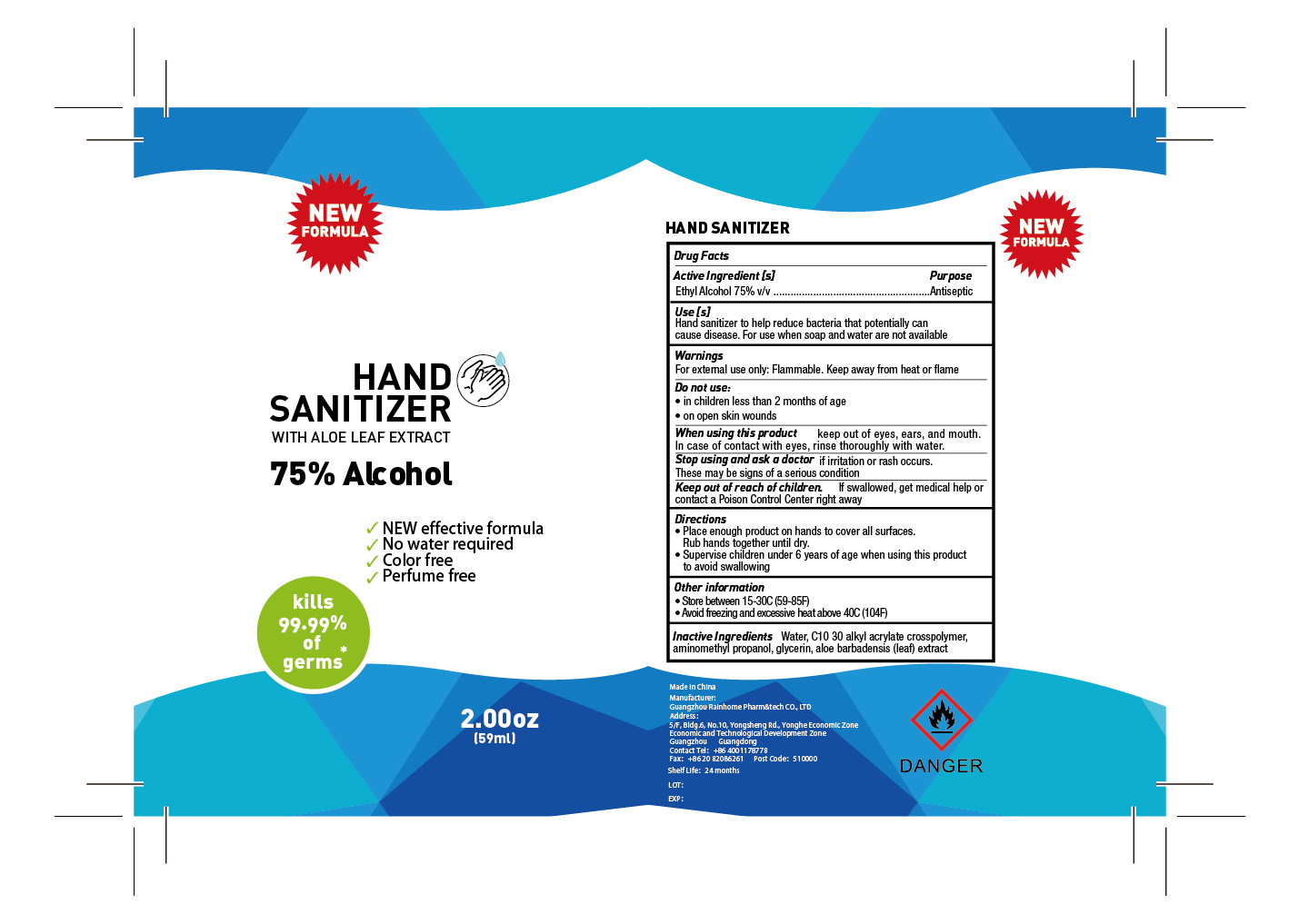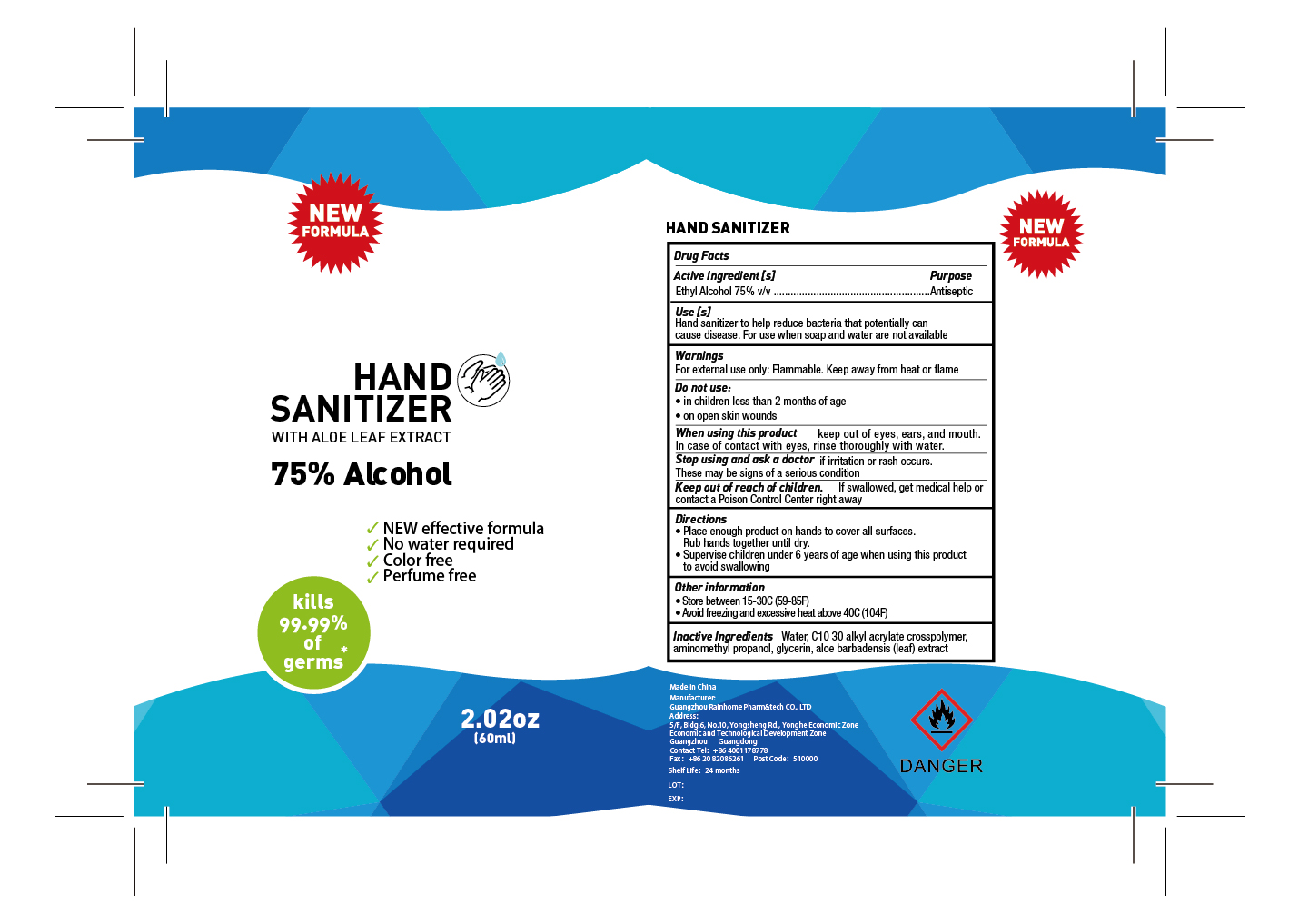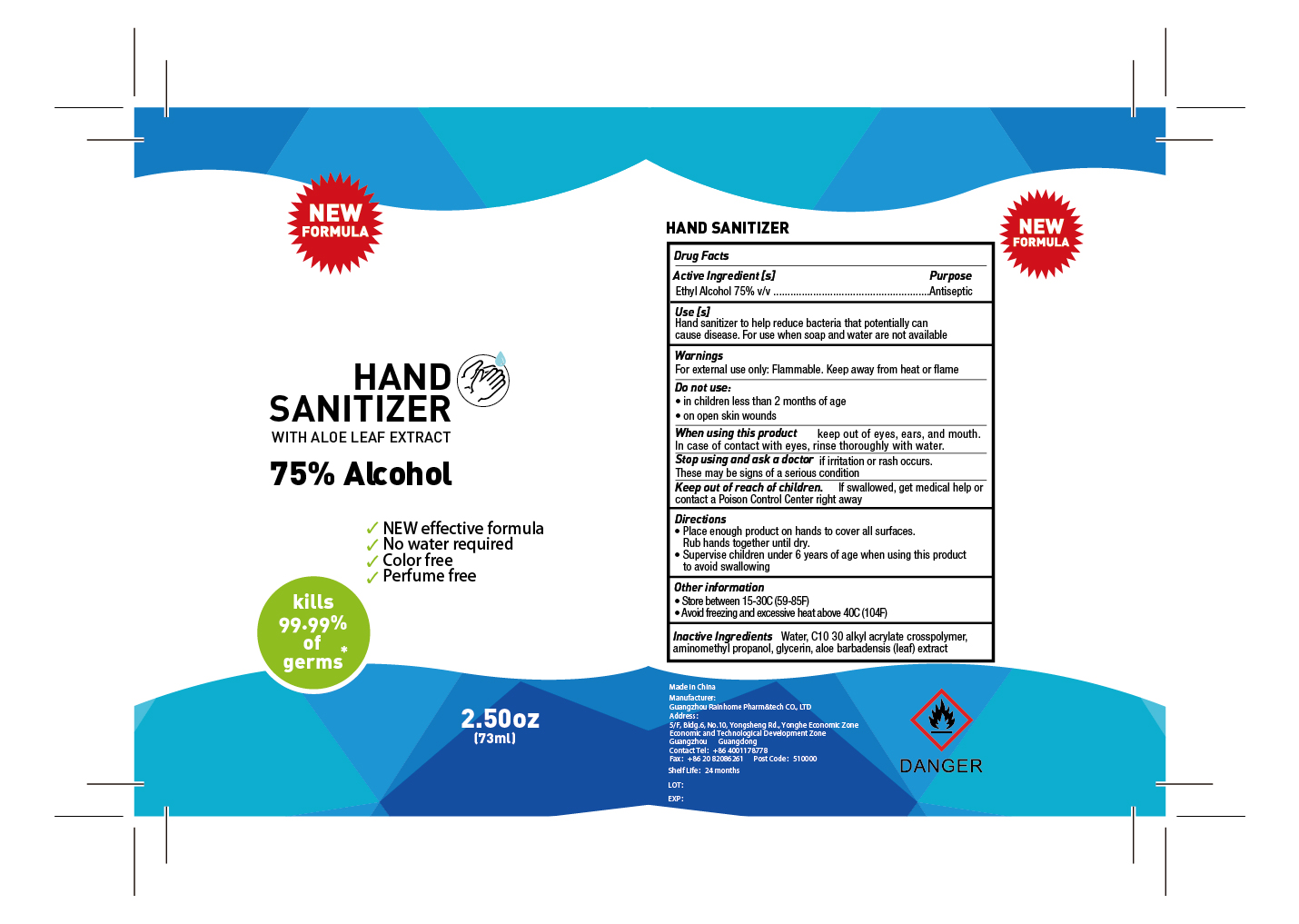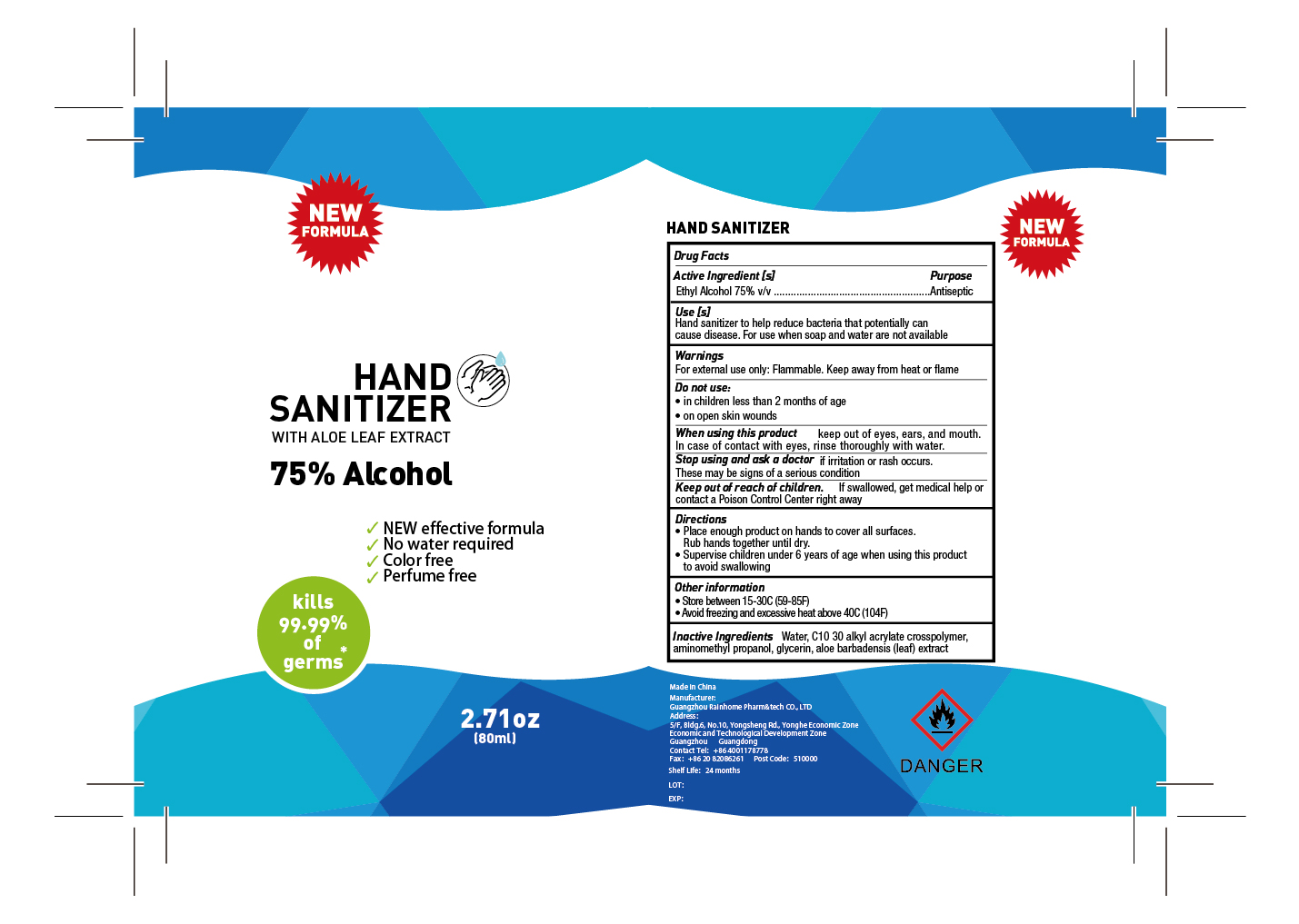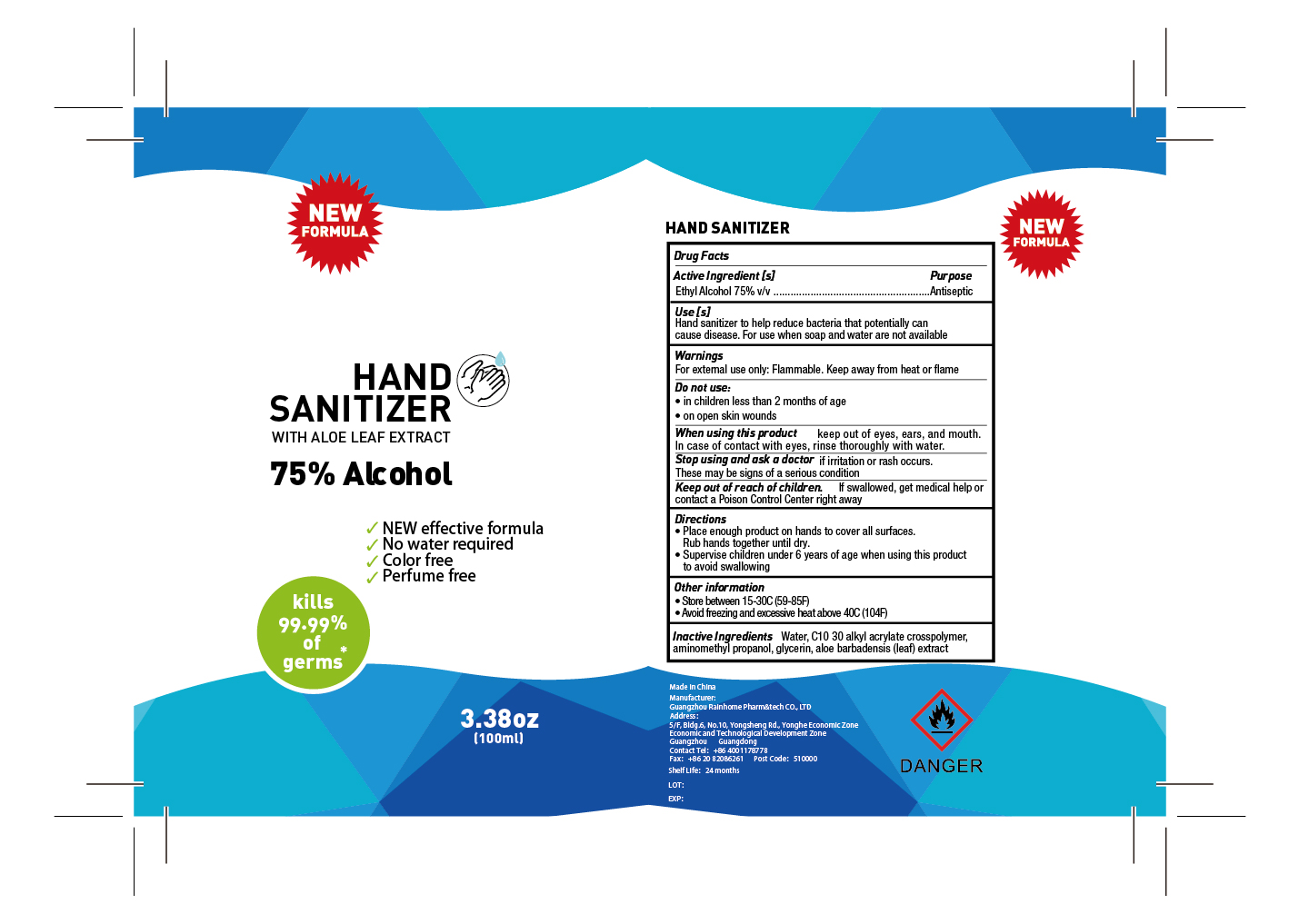 DRUG LABEL: Hand Sanitizer
NDC: 78126-007 | Form: GEL
Manufacturer: GUANGZHOU RAINHOME PHARM&TECH CO., LTD
Category: otc | Type: HUMAN OTC DRUG LABEL
Date: 20200514

ACTIVE INGREDIENTS: ALCOHOL 75 mL/100 mL
INACTIVE INGREDIENTS: GLYCERIN 0.5 mL/100 mL; CARBOMER COPOLYMER TYPE A (ALLYL PENTAERYTHRITOL CROSSLINKED) 0.4 mL/100 mL; WATER 24.05 mL/100 mL; AMINOMETHYLPROPANOL 0.04 mL/100 mL; ALOE VERA LEAF 0.01 mL/100 mL

Hand Sanitizer

Active Ingredient(s)

Ethyl Alcohol 75% v/

Purpose

Antiseptic

Use

Hand Sanitizer to help reduce bacteria that potentially can cause disease. For use when soap and water are not available.

Warnings

For external use only. Flammable. Keep away from heat or flame

Do not use

- in children less than 2 months of age
- on open skin wounds

WHEN USING

keep out of eyes, ears, and mouth. In case of contact with eyes, rinse eyes thoroughly with water

STOP USE

if irritation or rash occurs. These may be signs of a serious condition.

KEEP OUT OF REACH OF CHILDREN

If swallowed, get medical help or contact a Poison Control Center right away.

Directions

- Place enough product on hands to cover all surfaces. Rub hands together until dry.
- Supervise children under 6 years of age when using this product to avoid swallowing.

Other information

- Store between 15-30C (59-86F)
- Avoid freezing and excessive heat above 40C (104F)

Inactive ingredients

Water, C10 30 alkyl acrylate crosspolymer, aminomethyl propanol, glycerin, aloe barbadensis (leaf)extract